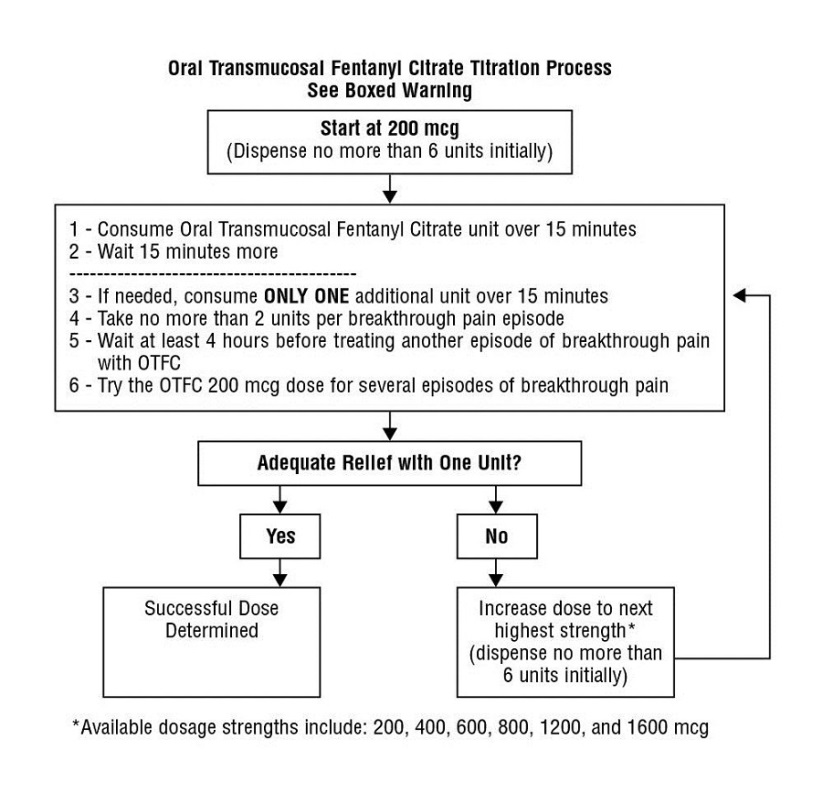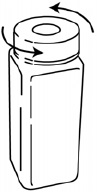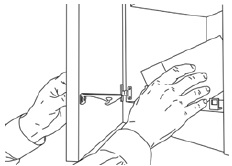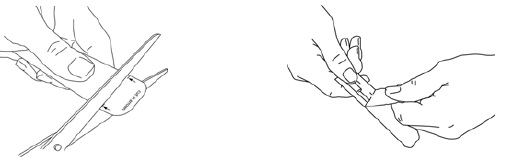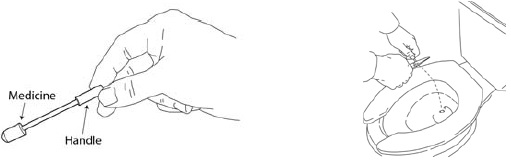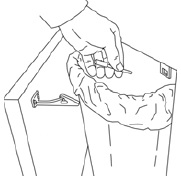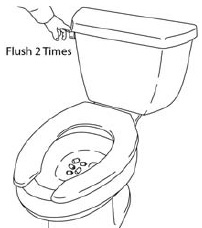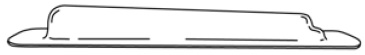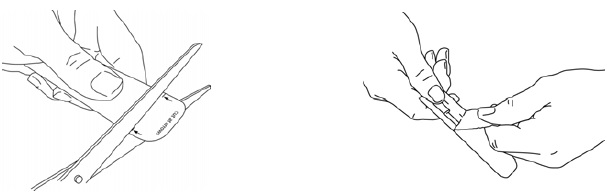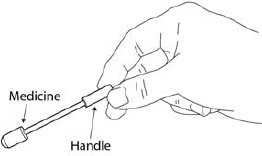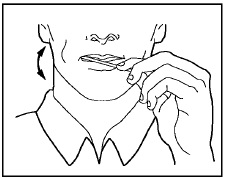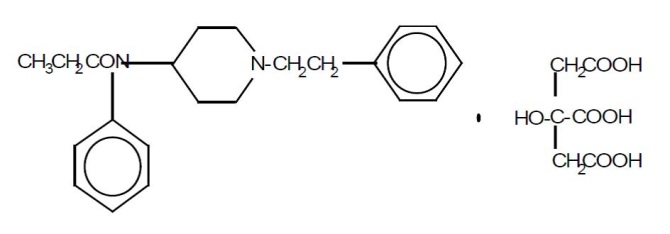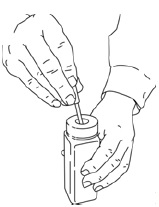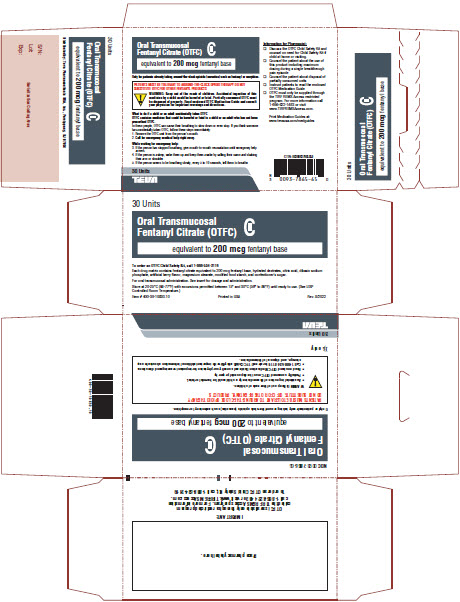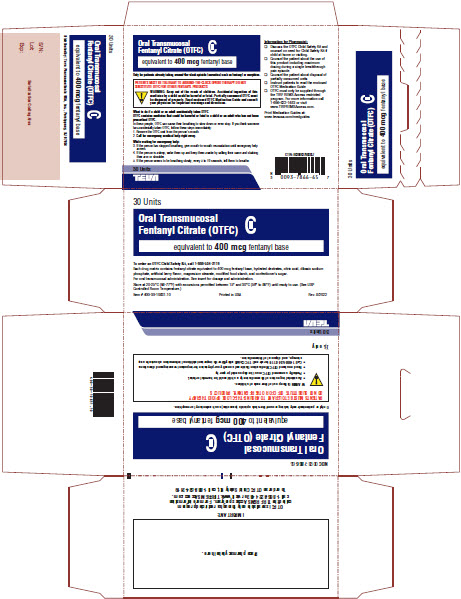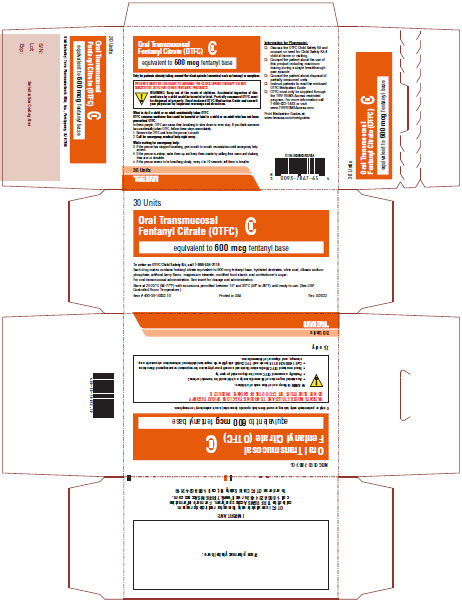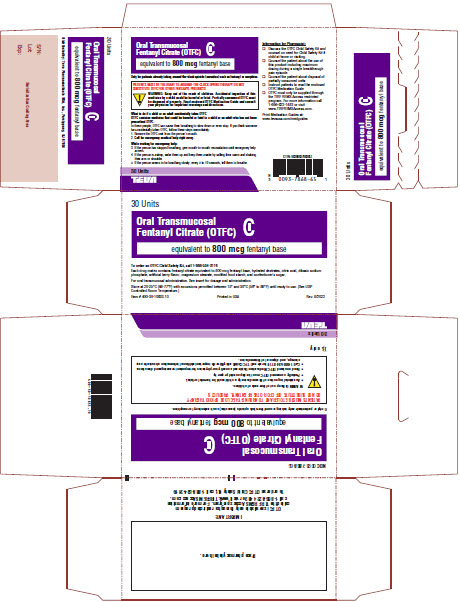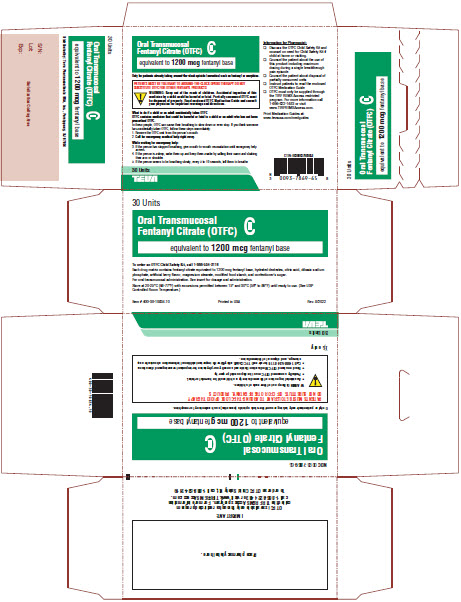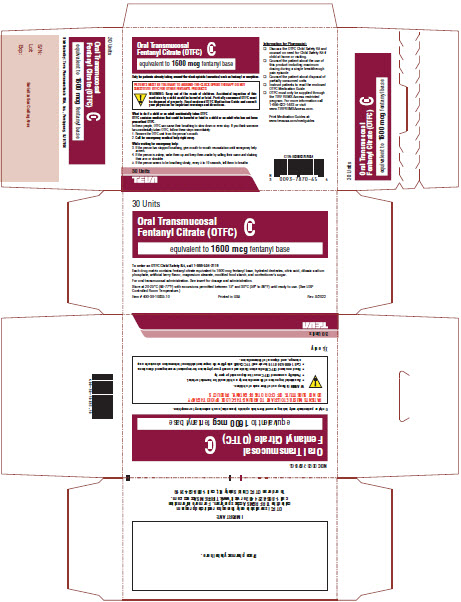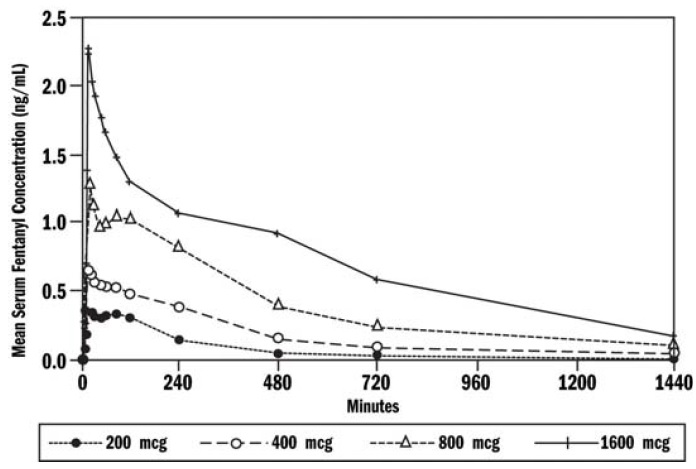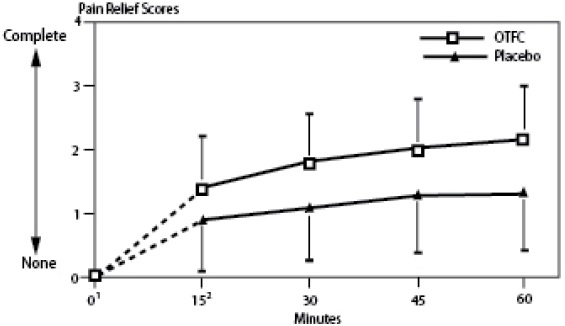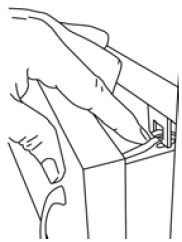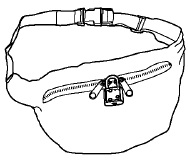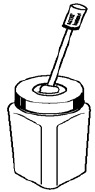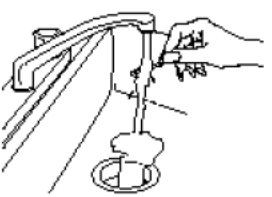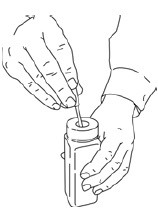 DRUG LABEL: Fentanyl Citrate
NDC: 0093-7865 | Form: LOZENGE
Manufacturer: Teva Pharmaceuticals USA, Inc.
Category: prescription | Type: HUMAN PRESCRIPTION DRUG LABEL
Date: 20260131
DEA Schedule: CII

ACTIVE INGREDIENTS: FENTANYL CITRATE 200 ug/1 1
INACTIVE INGREDIENTS: DEXTRATES; ANHYDROUS CITRIC ACID; SODIUM PHOSPHATE, DIBASIC, ANHYDROUS; MAGNESIUM STEARATE; MODIFIED CORN STARCH (1-OCTENYL SUCCINIC ANHYDRIDE); SUCROSE

HIGHLIGHTS OF PRESCRIBING INFORMATION

These highlights do not include all the information needed to use Oral Transmucosal Fentanyl Citrate (OTFC) safely and effectively. See full prescribing information for OTFC.
Oral Transmucosal Fentanyl Citrate (OTFC) (fentanyl citrate) oral transmucosal lozenge, CII
Initial U.S. Approval: 1968

RECENT MAJOR CHANGES

Boxed Warning 1/2026

Dosage and Administration (2.2) 1/2026

Warnings and Precautions (5.1, 5.2, 5.4, 5.15) 1/2026

WARNING: SERIOUS AND LIFE-THREATENING RISKS FROM USE OF ORAL TRANSMUCOSAL FENTANYL CITRATE (OTFC)

WARNING: SERIOUS AND LIFE-THREATENING RISKS FROM USE OF OTFC

See full prescribing information for complete boxed warning.

- OTFC exposes users to risks of addiction, abuse, and misuse, which can lead to overdose and death. Assess patient’s risk before prescribing and reassess regularly for these behaviors and conditions. (5.1)
- Serious, life-threatening, or fatal respiratory depression has occurred in patients treated with OTFC, including following use in opioid non-tolerant patients and improper dosing. Regularly evaluate patients, especially upon initiation or following a dosage increase. To reduce the risk of respiratory depression, proper dosing and titration of OTFC are essential. The substitution of OTFC for any other fentanyl product may result in fatal overdose. Due to the risk of fatal respiratory depression, OTFC is contraindicated in opioid non-tolerant patients and in management of acute or postoperative pain, including headache/migraines. (1, 4, 5.2)
- Accidental ingestion of OTFC, especially by children, can result in a fatal overdose of fentanyl. Keep out of reach of children. Ensure proper storage and disposal. (2.8, 5.3)
- Concomitant use of opioids with benzodiazepines or other central nervous system (CNS) depressants, including alcohol, may result in profound sedation, respiratory depression, coma, and death. Reserve concomitant prescribing for use in patients for whom alternative treatment options are inadequate. (5.4, 7)
- Advise pregnant women using opioids for an extended period of time of the risk of Neonatal Opioid Withdrawal Syndrome, which may be life-threatening if not recognized and treated. Ensure that management by neonatology experts will be available at delivery. (5.8)
- OTFC is available only through a restricted program called the TIRF REMS. Pharmacies, outpatients, and healthcare professionals who prescribe to outpatients are required to enroll in the program. Patients must be opioid tolerant to receive a TIRF medicine (5.7)
- When prescribing, do not convert patients on a mcg per mcg basis from any other fentanyl product to OTFC. (5.5)
- When dispensing, do not substitute with any other fentanyl products. (5.5)
- Concomitant use with CYP3A4 inhibitors (or discontinuation of CYP3A4 inducers) can result in a fatal overdose of fentanyl. (5.6, 7, 12.3)

1 INDICATIONS AND USAGE

OTFC is an opioid agonist indicated for the management of breakthrough pain in cancer patients 16 years of age and older who are already receiving and who are tolerant to around-the-clock opioid therapy for their underlying persistent cancer pain. (1)

Patients considered opioid tolerant are those who are taking, for one week or longer, around-the-clock medicine consisting of at least 60 mg of oral morphine per day, at least 25 mcg of transdermal fentanyl per hour, at least 30 mg of oral oxycodone per day, at least 8 mg of oral hydromorphone per day, at least 25 mg oral oxymorphone per day, at least 60 mg of oral hydrocodone per day, or an equianalgesic dose of another opioid. Patients must remain on around-the-clock opioids while taking OTFC.

Limitations of Use:

- Not for use in opioid non-tolerant patients.
- Not for use in the management of acute or postoperative pain, including headache/migraine or dental pain. (4)
- As a part of the TIRF REMS, OTFC may be dispensed by outpatient pharmacies only to outpatients enrolled in the program. (5.7) For inpatient administration of OTFC, patient and prescriber enrollment are not required.

2 DOSAGE AND ADMINISTRATION

- Patients must require and use around-the-clock opioids when taking OTFC. (1)
- OTFC should be prescribed only by healthcare professionals who are knowledgeable about the use of opioids and how to mitigate the associated risks. (2.1)
- Use the lowest effective dosage for the shortest duration of time consistent with individual patient treatment goals. Reserve titration to higher doses of OTFC for patients in whom lower doses are insufficiently effective and in whom the expected benefits of using a higher dose opioid clearly outweigh the substantial risks. (2.1, 5)
- Initiate the dosing regimen for each patient individually, taking into account the patient’s underlying cause and severity of pain, patient response, prior analgesic experience, and risk factors for addiction, abuse, and misuse. (2.1, 5.1)
- Respiratory depression can occur at any time during opioid therapy, especially when initiating and following dosage increases with OTFC. Consider this risk when selecting an initial dose and when making dose adjustments. (2.1, 5.2)
- Discuss opioid overdose reversal agents and options for acquiring them with the patient and/or caregiver both when initiating and renewing treatment with OTFC, especially if the patient has additional risk factors for overdose, or close contacts at risk for exposure and overdose. (2.2, 5.1, 5.2, 5.4)
- Initial dose of OTFC: 200 mcg. Prescribe an initial supply of six 200 mcg OTFC units. (2.3)
- Individually titrate to a tolerable dose that provides adequate analgesia using single OTFC dosage unit per breakthrough cancer pain episode. (2.4)
- No more than two doses can be taken per breakthrough pain episode. (2.4, 2.5)
- Wait at least 4 hours before treating another episode of breakthrough pain with OTFC. (2.4, 2.5)
- Limit consumption to four or fewer units per day once successful dose is found. (2.5)
- Periodically reassess patients receiving OTFC to evaluate the continued need for opioid analgesics to maintain pain control, for the signs or symptoms of adverse reactions, and for the development of addiction, abuse, or misuse. (2.5)
- When opioid therapy is no longer required, consider discontinuing OTFC along with a gradual downward of other opioids to minimize possible withdrawal effects. (2.7)

3 DOSAGE FORMS AND STRENGTHS

- Solid oral transmucosal lozenge: 200 mcg, 400 mcg, 600 mcg, 800 mcg, 1200 mcg, and 1600 mcg. (3)

4 CONTRAINDICATIONS

- Opioid non-tolerant patients. (4)
- Significant respiratory depression. (4)
- Management of acute or postoperative pain, including headache/migraine and dental pain. (4)
- Acute or severe bronchial asthma in an unmonitored setting or in absence of resuscitative equipment. (4)
- Known or suspected gastrointestinal obstruction, including paralytic ileus. (4)
- Known hypersensitivity to fentanyl or components of OTFC. (4)

5 WARNINGS AND PRECAUTIONS

- Opioid-Induced Hyperalgesia and Allodynia: Opioid-Induced Hyperalgesia (OIH) occurs when an opioid analgesic paradoxically causes an increase in pain, or an increase in sensitivity to pain. If OIH is suspected, carefully consider appropriately decreasing the dose of the current opioid analgesic or opioid rotation. (5.9)
- Serotonin Syndrome: Potentially life-threatening condition could result from concomitant serotonergic drug administration. Discontinue OTFC if serotonin syndrome is suspected. (5.10)
- Life-Threatening Respiratory Depression in Patients with Chronic Pulmonary Disease or in Elderly, Cachectic, or Debilitated Patients: Regularly evaluate patients, particularly during initiation and titration. (5.11)
- Adrenal Insufficiency: If diagnosed, treat with physiologic replacement of corticosteroids, and wean patient off of the opioid. (5.12)
- Severe Hypotension: Regularly evaluate patients during dosage initiation and titration. Avoid use of OTFC in patients with circulatory shock. (5.13)
- Risks of Use in Patients with Increased Intracranial Pressure, Brain Tumors, Head Injury, or Impaired Consciousness: Monitor for sedation and respiratory depression. Avoid use of OTFC in patients with impaired consciousness or coma. (5.14)

6 ADVERSE REACTIONS

Most common (frequency ≥5%): nausea, dizziness, somnolence, vomiting, asthenia, and headache, dyspnea, constipation, anxiety, confusion, depression, rash, and insomnia. (6.1)

To report SUSPECTED ADVERSE REACTIONS, contact Teva Pharmaceuticals at 1-888-483-8279 or FDA at 1-800-FDA-1088 or www.fda.gov/medwatch.

7 DRUG INTERACTIONS

- Mixed Agonist/Antagonist and Partial Agonist Opioid Analgesics: Avoid the use of mixed agonist/antagonist or partial agonist analgesics in patients who are already receiving a full opioid agonist analgesic (including OTFC) because they may reduce analgesic effect of OTFC or precipitate withdrawal symptoms. (7)

8 USE IN SPECIFIC POPULATIONS

- Pregnancy: May cause fetal harm. (8.1)
- Lactation: Not recommended. (8.2)
- Renal and Hepatic Impairment: Administer OTFC with caution. (8.6)

FULL PRESCRIBING INFORMATION

WARNING: SERIOUS AND LIFE-THREATENING RISKS FROM USE OF ORAL TRANSMUCOSAL FENTANYL CITRATE (OTFC)

Addiction, Abuse, and Misuse

Because the use of OTFC exposes patients and other users to the risks of opioid addiction, abuse, and misuse, which can lead to overdose and death, assess each patient’s risk prior to prescribing and reassess all patients regularly for the development of these behaviors and conditions [see Warnings and Precautions (5.1)].

Life-Threatening Respiratory Depression

Serious, life-threatening, or fatal respiratory depression has occurred in patients treated with Oral Transmucosal Fentanyl Citrate (OTFC), including following use in opioid non-tolerant patients and improper dosing. Evaluate patients for respiratory depression, especially during initiation of OTFC or following a dosage increase. To reduce the risk of respiratory depression, proper dosing and titration of OTFC are essential. The substitution of OTFC for any other fentanyl product may result in fatal overdose [see Warnings and Precautions (5.2)].

Due to the risk of respiratory depression, OTFC is contraindicated in the management of acute or postoperative pain including headache/migraine and in opioid non-tolerant patients [see Contraindications (4)].

Accidental Ingestion

Accidental ingestion of even one dose of OTFC, especially by children, can result in a fatal overdose of fentanyl. Death has been reported in children who have accidentally ingested OTFC. OTFC must be kept out of reach of children [see Warnings and Precautions (5.3)].

Risks From Concomitant Use with Benzodiazepines or Other CNS Depressants

Concomitant use of opioids with benzodiazepines or other central nervous system (CNS) depressants, including alcohol, may result in profound sedation, respiratory depression, coma, and death. Reserve concomitant prescribing of OTFC and benzodiazepines or other CNS depressants for use in patients for whom alternative treatment options are inadequate [see Warnings and Precautions (5.4), Drug Interactions (7)].

Risk of Medication Errors

Substantial differences exist in the pharmacokinetic profile of OTFC compared to other fentanyl products that result in clinically important differences in the extent of absorption of fentanyl and that could result in fatal overdose [see Dosage and Administration (2.1), Warnings and Precautions (5.5)].

- When prescribing, do not convert patients on a mcg per mcg basis from any other fentanyl products to OTFC [see Dosage and Administration (2.1)].
- When dispensing, do not substitute an OTFC prescription for other fentanyl products.

Cytochrome P450 3A4 Interaction

The concomitant use of OTFC with all cytochrome P450 3A4 inhibitors may result in an increase in fentanyl plasma concentrations, which could increase or prolong adverse reactions and may cause potentially fatal respiratory depression. In addition, discontinuation of a concomitantly used cytochrome P450 3A4 inducer may result in an increase in fentanyl plasma concentration. Evaluate patients at frequent intervals receiving OTFC and any CYP3A4 inhibitor or inducer [see Warnings and Precautions (5.6), Drug Interactions (7), Clinical Pharmacology (12.3)].

Risk Evaluation and Mitigation Strategy (REMS)

Because of the risk for accidental exposure, misuse, abuse, addiction, and overdose, OTFC is available only through a restricted program required by the Food and Drug Administration, called a Risk Evaluation and Mitigation Strategy (REMS). Under the Transmucosal Immediate Release Fentanyl (TIRF) REMS, pharmacies, outpatients, and healthcare professionals who prescribe to outpatients must enroll in the program. Inpatient pharmacies must develop policies and procedures to verify opioid tolerance in inpatients who require OTFC while hospitalized. Further information is available at www.TIRFREMSAccess.com or by calling 1-866-822-1483 [see Warnings and Precautions (5.7)].

Neonatal Opioid Withdrawal Syndrome (NOWS)

Advise pregnant women using opioids for an extended period of time of the risk of Neonatal Opioid Withdrawal Syndrome, which may be life-threatening if not recognized and treated. Ensure that management by neonatology experts will be available at delivery [see Warnings and Precautions (5.8)].

1 INDICATIONS AND USAGE

Oral Transmucosal Fentanyl Citrate (OTFC) is indicated for the management of breakthrough pain in cancer patients 16 years of age and older who are already receiving and who are tolerant to around-the-clock opioid therapy for their underlying persistent cancer pain.

Patients considered opioid tolerant are those who are taking, for one week or longer, around-the-clock medicine consisting of at least 60 mg of oral morphine per day, at least 25 mcg of transdermal fentanyl per hour, at least 30 mg of oral oxycodone per day, at least 8 mg of oral hydromorphone per day, at least 25 mg oral oxymorphone per day, at least 60 mg of oral hydrocodone per day, or an equianalgesic dose of another opioid. Patients must remain on around-the-clock opioids when taking OTFC.

Limitations of Use:

- Not for use in opioid non-tolerant patients.
- Not for use in the management of acute or postoperative pain, including headache/migraine and dental pain [see Contraindications (4)].
- As a part of the TIRF REMS, OTFC may be dispensed by outpatient pharmacies only to outpatients enrolled in the program [see Warnings and Precautions (5.7)]. For inpatient administration of OTFC, patient and prescriber enrollment are not required.

2 DOSAGE AND ADMINISTRATION

2.1 Important Dosage and Administration Instructions

- Healthcare professionals who prescribe Oral Transmucosal Fentanyl Citrate (OTFC) for outpatients must enroll in the TIRF REMS and comply with the requirements of the REMS to ensure safe use of OTFC [see Warnings and Precautions (5.7)].
- Use the lowest effective dosage for the shortest duration consistent with individual patient treatment goals [see Warnings and Precautions (5)]. Because the risk of overdose increases as opioid doses increase, reserve titration to higher doses of OTFC for patients in whom lower doses are insufficiently effective and in whom the expected benefits of using a higher dose opioid clearly outweigh the substantial risks.
- It is important to minimize the number of strengths available to patients at any time to prevent confusion and possible overdose.
- There is variability in the opioid analgesic dose and duration needed to adequately manage pain due both to the cause of pain and to individual patient factors. Initiate the dosing regimen for each patient individually, taking into account the patient's severity of pain, patient response, prior analgesic treatment experience, and risk factors for addiction, abuse, and misuse [see Warnings and Precautions (5.1)].
- Respiratory depression can occur at any time during opioid therapy, especially when initiating and following dosage increases with OTFC. Consider this risk when selecting an initial dose and when making dose adjustments [see Warnings and Precautions (5)].
- Instruct patients and caregivers to take steps to store OTFC securely and to properly dispose of unused OTFC as soon as no longer needed [see Warnings and Precautions (5.1, 5.3)].
- Other TIRF formulations and OTFC are not equivalent. DO NOT substitute an OTFC prescription for any other TIRF formulation under any circumstances. Do not convert patients on a mcg per mcg basis from any other fentanyl product to OTFC [see Warnings and Precautions (5.5)].

2.2 Patient Access to an Opioid Overdose Reversal Agent for the Emergency Treatment of Opioid Overdose

Inform patients and caregivers about opioid overdose reversal agents (e.g., naloxone, nalmefene). Discuss the importance of having access to an opioid overdose reversal agent, especially if the patient has risk factors for overdose (e.g., concomitant use of CNS depressants, a history of opioid use disorder, or prior opioid overdose) or if there are household members (including children) or other close contacts at risk for accidental ingestion or opioid overdose. The presence of risk factors for overdose should not prevent the management of pain in any patient [see Warnings and Precautions (5.1, 5.2, 5.4)].

Discuss the options for obtaining an opioid overdose reversal agent (e.g., prescription, over-the-counter, or as part of a community-based program) [see Warnings and Precautions (5.2)].

There are important differences among the opioid overdose reversal agents, such as route of administration, product strength, approved patient age range, and pharmacokinetics. Be familiar with these differences, as outlined in the approved labeling for those products, prior to recommending or prescribing such an agent.

2.3 Initial Dosage

Individually titrate OTFC to a dose that provides adequate analgesia and minimizes side effects. The initial dose of OTFC to treat episodes of breakthrough cancer pain is always 200 mcg. The OTFC unit should be consumed over 15 minutes. Patients should be prescribed an initial titration supply of six 200 mcg OTFC units, thus limiting the number of units in the home during titration. Patients should use up all units before increasing to a higher dose to prevent confusion and possible overdose.

Repeat Dosing

1. In cases where the breakthrough pain episode is not relieved after 15 minutes after completion of the OTFC unit (30 minutes after the start of the unit), patients may take ONLY ONE additional dose using the same strength for that episode. Thus patients should take a maximum of two doses of OTFC for any episode of breakthrough pain.
2. Patients MUST wait at least 4 hours before treating another episode of breakthrough pain with OTFC.

2.4 Dose Titration

From an initial dose, closely follow patients and change the dosage strength until the patient reaches a dose that provides adequate analgesia using a single OTFC dosage unit per breakthrough cancer pain episode. If signs of excessive opioid effects appear before the unit is consumed, the dosage unit should be removed from the patient’s mouth immediately, disposed of properly, and subsequent doses should be decreased. Patients should record their use of OTFC over several episodes of breakthrough cancer pain and review their experience with their healthcare providers to determine if a dosage adjustment is warranted.

In cases where the breakthrough pain episode is not relieved 15 minutes after completion of the OTFC unit (30 minutes after the start of the unit), patients may take ONLY ONE additional dose of the same strength for that episode. Thus, patients should take a maximum of two doses of OTFC for any breakthrough pain episode.

Patients must wait at least 4 hours before treating another episode of breakthrough pain with OTFC. To reduce the risk of overdosing during titration, patients should have only one strength of OTFC available at any one time.

2.5 Maintenance Dosing

1. Once titrated to an effective dose, patients should generally use ONLY ONE OTFC unit of the appropriate strength per breakthrough pain episode.
2. On those occasions when the breakthrough pain episode is not relieved 15 minutes after completion of the OTFC unit, patient may take ONLY ONE additional dose using the same strength for that episode.
3. Patients MUST wait at least 4 hours before treating another episode of breakthrough pain with OTFC. Once a successful dose has been found (i.e., an average episode is treated with a single unit), patients should limit consumption to four or fewer units per day.
4. Dosage adjustment of OTFC may be required in some patients in order to continue to provide adequate relief of breakthrough pain. If after increasing the dosage, unacceptable opioid-related adverse reactions are observed (including an increase in pain after dosage increase), consider reducing the dosage [see Warnings and Precautions (5)]. Adjust the dosage to obtain an appropriate balance between management of pain and opioid-related adverse reactions.
5. Generally, the OTFC dose should be increased only when a single administration of the current dose fails to adequately treat the breakthrough pain episode for several consecutive episodes.
6. If the patient experiences greater than four breakthrough pain episodes per day, the dose of the maintenance (around-the-clock) opioid used for persistent pain should be re-evaluated.

2.6 Administration of OTFC

Open the blister package with scissors immediately prior to product use. The patient should place the OTFC unit in his or her mouth between the cheek and lower gum, occasionally moving the drug matrix from one side to the other using the handle. The OTFC unit should be sucked, not chewed. A unit dose of OTFC, if chewed and swallowed, might result in lower peak concentrations and lower bioavailability than when consumed as directed [see Clinical Pharmacology (12.3)].

The OTFC unit should be consumed over a 15-minute period. Longer or shorter consumption times may produce less efficacy than reported in OTFC clinical trials. If signs of excessive opioid effects appear before the unit is consumed, remove the drug matrix from the patient’s mouth immediately and decrease future doses.

2.7 Discontinuation of OTFC

When opioid therapy is no longer required, consider discontinuing OTFC along with a gradual downward tapering (titration) of other opioids to minimize possible withdrawal effects. In patients who continue to take their chronic opioid therapy for persistent pain but no longer require treatment for breakthrough pain, OTFC therapy can usually be discontinued immediately [see Drug Abuse and Dependence (9.3)].

2.8 Disposal of OTFC

After consumption of the unit is complete and the matrix is totally dissolved, throw away the handle in a trash container that is out of the reach of children.

- If any of the drug matrix remains on the handle, place the handle under hot running tap water until all of the drug matrix is dissolved, and then dispose of the handle in a place that is out of the reach of children.
- Dispose of handles in the child-resistant container (as described in steps 1 and 2) at least once a day.

If the temporary storage bottle provided as part of the OTFC Child Safety Kit is available, partially consumed units may be stored in the specially provided child-resistant container out of the reach of children until proper disposal is possible.

Unopened units remaining from a prescription must be properly disposed as soon as they are no longer needed.

To dispose of the unused OTFC units:

- Remove the OTFC unit from its blister package using scissors, and hold OTFC by its handle over the toilet bowl.
- Using wire-cutting pliers cut off the drug matrix end so that it falls into the toilet.
- Dispose of the handle in a place that is out of the reach of children.
- Repeat steps 1, 2, and 3 for each OTFC unit. Flush the toilet twice after 5 units have been cut and deposited into the toilet.

Do not flush the entire OTFC units, OTFC handles, blister packages, or cartons down the toilet. Dispose of the handle where children cannot reach it.

In the event that a caregiver requires additional assistance in disposing of excess unusable units that remain in the home after a patient has expired, instruct them to call the toll-free number for Teva Pharmaceuticals (1-888-483-8279) or seek assistance from their local DEA office.

3 DOSAGE FORMS AND STRENGTHS

Solid oral transmucosal lozenge: Each dosage unit has white to off-white color and is a solid drug matrix on a handle. Each strength is marked on the individual solid drug matrix and the handle tag. Oral Transmucosal Fentanyl Citrate (OTFC) is available in 200 mcg, 400 mcg, 600 mcg, 800 mcg, 1200 mcg and 1600 mcg strengths [see How Supplied/Storage and Handling (16)].

4 CONTRAINDICATIONS

Oral Transmucosal Fentanyl Citrate (OTFC) is contraindicated in:

- Opioid non-tolerant patients: Life-threatening respiratory depression and death could occur at any dose in opioid non-tolerant patients [see Indications and Usage (1), Warnings and Precautions (5.2)].
- Significant respiratory depression [see Warnings and Precautions (5.2)].
- Acute or postoperative pain including headache/migraine and dental pain, or acute pain in the emergency department [see Indications and Usage (1)].
- Acute or severe bronchial asthma in an unmonitored setting or in the absence of resuscitative equipment [see Warnings and Precautions (5.11)].
- Known or suspected gastrointestinal obstruction, including paralytic ileus [see Warnings and Precautions (5.15)].
- Known hypersensitivity to fentanyl or components of OTFC (e.g., anaphylaxis, hypersensitivity) [see Adverse Reactions (6.2)].

5 WARNINGS AND PRECAUTIONS

5.1 Addiction, Abuse, and Misuse

Oral Transmucosal Fentanyl Citrate (OTFC) contains fentanyl, a Schedule II controlled substance. As an opioid, OTFC exposes users to the risks of addiction, abuse, and misuse [see Drug Abuse and Dependence (9)].

Although the risk of addiction in any individual is unknown, it can occur in patients appropriately prescribed OTFC. Addiction can occur at recommended dosages and if the drug is misused or abused. The risk of opioid-related overdose or overdose-related death is increased with higher opioid doses, and this risk persists over the course of therapy. In postmarketing studies, addiction, abuse, misuse, and fatal and non-fatal opioid overdose were observed in patients with long-term opioid use [see Adverse Reactions (6.2)].

Assess each patient’s risk for opioid addiction, abuse, or misuse prior to prescribing OTFC, and reassess all patients receiving OTFC for the development of these behaviors and conditions. Risks are increased in patients with a personal or family history of substance abuse (including drug or alcohol abuse or addiction) or mental illness (e.g., major depression). The potential for these risks should not, however, prevent the proper management of pain in any given patient. Patients at increased risk may be prescribed opioids such as OTFC, but use in such patients necessitates intensive counseling about the risks and proper use of OTFC along with frequent reevaluation for signs of addiction, abuse, and misuse. Consider recommending or prescribing an opioid overdose reversal agent [see Dosage and Administration (2.2), Warnings and Precautions (5.2)].

Opioids are sought for nonmedical use and are subject to diversion from legitimate prescribed use. Consider these risks when prescribing or dispensing OTFC. Strategies to reduce these risks include prescribing the drug in the smallest appropriate quantity and advising the patient on careful storage of the drug during the course of treatment and proper disposal of unused drug. Contact local state professional licensing board or state-controlled substances authority for information on how to prevent and detect abuse or diversion of this product.

5.2 Life-Threatening Respiratory Depression

Serious, life-threatening, or fatal respiratory depression has been reported with the use of opioids, even when used as recommended. Respiratory depression, if not immediately recognized and treated, may lead to respiratory arrest and death. Management of respiratory depression may include close observation, supportive measures, and use of opioid overdose reversal agents, depending on the patient’s clinical status [see Overdosage (10)]. Carbon dioxide (CO2) retention from opioid-induced respiratory depression can exacerbate the sedating effects of opioids.

While serious, life-threatening, or fatal respiratory depression can occur at any time during the use of OTFC, the risk is greatest during the initiation of therapy or following a dosage increase.

To reduce the risk of respiratory depression, proper dosing and titration of OTFC are essential [see Dosage and Administration (2)]. Overestimating the OTFC dosage can result in a fatal overdose with the first dose. The substitution of OTFC for any other fentanyl product may result in fatal overdose [see Warnings and Precautions (5.5)].

OTFC could be fatal to individuals for whom it is not prescribed and for those who are not opioid-tolerant.

Accidental ingestion of even one dose of OTFC, especially by children, can result in respiratory depression and death due to an overdose of fentanyl [see Warnings and Precautions (5.3)].

Educate patients and caregivers on how to recognize respiratory depression and emphasize the importance of calling 911 or getting emergency medical help right away in the event of a known or suspected overdose.

Opioids can cause sleep-related breathing disorders including central sleep apnea (CSA) and sleep-related hypoxemia. Opioid use increases the risk of CSA in a dose-dependent fashion. In patients who present with CSA, consider decreasing the opioid dosage using best practices for opioid taper [see Dosage and Administration (2.7)].

Patient Access to an Opioid Overdose Reversal Agent for the Emergency Treatment of Opioid Overdose

Inform patients and caregivers about opioid overdose reversal agents (e.g., naloxone, nalmefene). Discuss the importance of having access to an opioid overdose reversal agent, especially if the patient has risk factors for overdose (e.g., concomitant use of CNS depressants, a history of opioid use disorder, or prior opioid overdose) or if there are household members (including children) or other close contacts at risk for accidental ingestion or opioid overdose. The presence of risk factors for overdose should not prevent the management of pain in any patient [see Warnings and Precautions (5.1, 5.4)].

Discuss the options for obtaining an opioid overdose reversal agent (e.g., prescription, over-the-counter, or as part of a community-based program).

There are important differences among the opioid overdose reversal agents, such as route of administration, product strength, approved patient age range, and pharmacokinetics. Be familiar with these differences, as outlined in the approved labeling for those products, prior to recommending or prescribing such an agent.

Educate patients and caregivers on how to recognize respiratory depression, and how to use an opioid overdose reversal agent for the emergency treatment of opioid overdose. Emphasize the importance of calling 911 or getting emergency medical help, even if an opioid overdose reversal agent is administered [see Dosage and Administration (2.2), Warnings and Precautions (5.1, 5.4), Overdosage (10)].

5.3 Increased Risk of Overdose in Children Due to Accidental Ingestion or Exposure

Death has been reported in children who have accidentally ingested OTFC.

Patients and their caregivers must be informed that OTFC contains a medicine in an amount which can be fatal to a child. Healthcare providers and dispensing pharmacists must specifically question patients or caregivers about the presence of children in the home (on a full time or visiting basis) and counsel them regarding the dangers to children from inadvertent exposure.

Patients and their caregivers must be instructed to keep both used and unused dosage units out of the reach of children. While all units should be disposed of immediately after use, partially consumed units represent a special risk to children. In the event that a unit is not completely consumed it must be properly disposed as soon as possible.

Detailed instructions for the proper storage, administration, disposal, and important instructions for managing an overdose of OTFC are provided in the OTFC Medication Guide. Encourage patients to read this information in its entirety and give them an opportunity to have their questions answered.

5.4 Risks from Concomitant Use with Benzodiazepines or Other CNS Depressants

Profound sedation, respiratory depression, coma, and death may result from the concomitant use of OTFC with benzodiazepines and/or other CNS depressants, including alcohol (e.g., non-benzodiazepine sedatives/hypnotics, anxiolytics, tranquilizers, muscle relaxants, general anesthetics, antipsychotics, gabapentinoids [gabapentin and pregabalin], and other opioids). Because of these risks, reserve concomitant prescribing of these drugs for use in patients for whom alternative treatment options are inadequate.

Observational studies have demonstrated that concomitant use of opioid analgesics and benzodiazepines increases the risk of drug-related mortality compared to use of opioid analgesics alone. Because of similar pharmacological properties, it is reasonable to expect similar risk with the concomitant use of other CNS depressant drugs with opioid analgesics [see Drug Interactions (7)].

If the decision is made to prescribe a benzodiazepine or other CNS depressant concomitantly with an opioid analgesic, prescribe the lowest effective dosages and minimum durations of concomitant use. In patients already receiving an opioid analgesic, prescribe a lower initial dose of the benzodiazepine or other CNS depressant than indicated in the absence of an opioid, and titrate based on clinical response. If an opioid analgesic is initiated in a patient already taking a benzodiazepine or other CNS depressant, prescribe a lower initial dose of the opioid analgesic, and titrate based on clinical response. Inform patients and caregivers of this potential interaction and educate them on the signs and symptoms of respiratory depression (including sedation).

If concomitant use is warranted, consider recommending or prescribing an opioid overdose reversal agent [see Dosage and Administration (2.2), Warnings and Precautions (5.2), Overdosage (10)].

Advise both patients and caregivers about the risks of respiratory depression and sedation when OTFC is used with benzodiazepines or other CNS depressants (including alcohol and illicit drugs). Advise patients not to drive or operate heavy machinery until the effects of concomitant use of the benzodiazepine or other CNS depressant have been determined. Screen patients for risk of substance use disorders, including opioid abuse and misuse, and warn them of the risk for overdose and death associated with the use of additional CNS depressants including alcohol and illicit drugs [see Drug Interactions (7)].

5.5 Risk of Medication Errors

When prescribing, do not convert a patient to OTFC from any other fentanyl product on a mcg per mcg basis as OTFC and other fentanyl products are not equivalent on a microgram per microgram basis.

OTFC is not a generic version of other transmucosal immediate release fentanyl (TIRF) formulations. When dispensing, do not substitute an OTFC prescription for any other TIRF formulation under any circumstances. Other TIRF formulations and OTFC are not equivalent. Substantial differences exist in the pharmacokinetic profile of OTFC compared to other fentanyl products including other TIRF formulations that result in clinically important differences in the rate and extent of absorption of fentanyl. As a result of these differences, the substitution of OTFC for any other fentanyl product may result in a fatal overdose.

There are no safe conversion directions available for patients on any other fentanyl products. (Note: This includes oral, transdermal, or parenteral formulations of fentanyl.) Therefore, for opioid tolerant patients, the initial dose of OTFC should always be 200 mcg. Each patient should be individually titrated to provide adequate analgesia while minimizing side effects [see Dosage and Administration (2.4)].

5.6 Risks of Concomitant Use or Discontinuation of Cytochrome P450 3A4 Inhibitors and Inducers

Concomitant use of OTFC with a CYP3A4 inhibitor, such as macrolide antibiotics (e.g., erythromycin), azole-antifungal agents (e.g., ketoconazole), and protease inhibitors (e.g., ritonavir), may increase plasma concentrations of fentanyl and prolong opioid adverse reactions, which may cause potentially fatal respiratory depression [see Warnings and Precautions (5.2)], particularly when an inhibitor is added after a stable dose of OTFC is achieved. Similarly, discontinuation of a CYP3A4 inducer, such as rifampin, carbamazepine, and phenytoin, in OTFC-treated patients may increase fentanyl plasma concentrations and prolong opioid adverse reactions. When using OTFC with CYP3A4 inhibitors or discontinuing CYP3A4 inducers in OTFC-treated patients, evaluate patients at frequent intervals and consider dosage reduction of OTFC until stable drug effects are achieved [see Drug Interactions (7)].

Concomitant use of OTFC with CYP3A4 inducers or discontinuation of a CYP3A4 inhibitor could decrease fentanyl plasma concentrations, decrease opioid efficacy or, possibly, lead to a withdrawal syndrome in a patient who had developed physical dependence to fentanyl. When using OTFC with CYP3A4 inducers or discontinuing CYP3A4 inhibitors, evaluate patients at frequent intervals and consider increasing the opioid dosage if needed to maintain adequate analgesia or if symptoms of opioid withdrawal occur [see Drug Interactions (7)].

5.7 Transmucosal Immediate Release Fentanyl (TIRF) Risk Evaluation and Mitigation Strategy (REMS)

Because of the risk for accidental exposure, misuse, abuse, addiction, and overdose [see Warnings and Precautions (5.1), Drug Abuse and Dependence (9)], OTFC is available only through a restricted program called the TIRF REMS. Under the TIRF REMS, healthcare professionals who prescribe to outpatients, the outpatients themselves, and pharmacies are required to enroll in the program.

Notable requirements of the TIRF REMS are:

- Prescribers for outpatient use must be certified with the REMS program by enrolling and completing training. Prescribers must document opioid tolerance with every OTFC prescription.
- Outpatients must be enrolled in the REMS program and must be opioid-tolerant to receive OTFC [see Dosage and Administration (2.1)].
- Outpatient pharmacies must be certified with the REMS program and verify documentation of opioid tolerance with every OTFC prescription.
- Inpatient pharmacies must be certified with the REMS program and develop policies and procedures to verify opioid tolerance in inpatients who require OTFC while hospitalized.
- Wholesalers and distributors must enroll in the REMS program and distribute only to certified pharmacies.

Further information, including a list of certified pharmacies and enrolled distributors, is available at www.TIRFREMSAccess.com or by calling 1-866-822-1483.

5.8 Neonatal Opioid Withdrawal Syndrome

Use of OTFC for an extended period of time during pregnancy can result in withdrawal in the neonate. Neonatal opioid withdrawal syndrome, unlike opioid withdrawal syndrome in adults, may be life-threatening if not recognized and treated, and requires management according to protocols developed by neonatology experts. Observe newborns for signs of neonatal opioid withdrawal syndrome and manage accordingly. Advise pregnant women using opioids for an extended period of time of the risk of neonatal opioid withdrawal syndrome and ensure that appropriate treatment will be available [see Use in Specific Populations (8.1)].

5.9 Opioid-Induced Hyperalgesia and Allodynia

Opioid-Induced Hyperalgesia (OIH) occurs when an opioid analgesic paradoxically causes an increase in pain, or an increase in sensitivity to pain. This condition differs from tolerance, which is the need for increasing doses of opioids to maintain a defined effect [see Dependence (9.3)]. Symptoms of OIH include (but may not be limited to) increased levels of pain upon opioid dosage increase, decreased levels of pain upon opioid dosage decrease, or pain from ordinarily non-painful stimuli (allodynia). These symptoms may suggest OIH only if there is no evidence of underlying disease progression, opioid tolerance, opioid withdrawal, or addictive behavior.

Cases of OIH have been reported, both with short-term and longer-term use of opioid analgesics. Though the mechanism of OIH is not fully understood, multiple biochemical pathways have been implicated. Medical literature suggests a strong biologic plausibility between opioid analgesics and OIH and allodynia. If a patient is suspected to be experiencing OIH, carefully consider appropriately decreasing the dose of the current opioid analgesic or opioid rotation (safely switching the patient to a different opioid moiety) [see Dosage and Administration (2.7)].

5.10 Serotonin Syndrome with Concomitant Use of Serotonergic Drugs

Cases of serotonin syndrome, a potentially life-threatening condition, have been reported during concomitant use of OTFC with serotonergic drugs. Serotonergic drugs include selective serotonin reuptake inhibitors (SSRIs), serotonin and norepinephrine reuptake inhibitors (SNRIs), tricyclic antidepressants (TCAs), triptans, 5-HT3 receptor antagonists, drugs that affect the serotonergic neurotransmitter system (e.g., mirtazapine, trazodone, tramadol), certain muscle relaxants (i.e., cyclobenzaprine, metaxalone), and drugs that impair metabolism of serotonin (including MAO inhibitors, both those intended to treat psychiatric disorders and also others, such as linezolid and intravenous methylene blue) [see Drug Interactions (7)]. This may occur within the recommended dosage range.

Serotonin syndrome symptoms may include mental status changes (e.g., agitation, hallucinations, coma), autonomic instability (e.g., tachycardia, labile blood pressure, hyperthermia), neuromuscular aberrations (e.g., hyperreflexia, incoordination, rigidity), and/or gastrointestinal symptoms (e.g., nausea, vomiting, diarrhea) and can be fatal. The onset of symptoms generally occurs within several hours to a few days of concomitant use, but may occur later than that. Discontinue OTFC if serotonin syndrome is suspected.

5.11 Life-Threatening Respiratory Depression in Patients with Chronic Pulmonary Disease or in Elderly, Cachectic, or Debilitated Patients

The use of OTFC in patients with acute or severe bronchial asthma in an unmonitored setting or in the absence of resuscitative equipment is contraindicated.

Patients with Chronic Pulmonary Disease: OTFC-treated patients with significant chronic obstructive pulmonary disease or cor pulmonale, and those with a substantially decreased respiratory reserve, hypoxia, hypercapnia, or pre-existing respiratory depression are at increased risk of decreased respiratory drive including apnea, even at recommended dosages of OTFC [see Warnings and Precautions (5.2)].

Elderly, Cachectic, or Debilitated Patients: Life-threatening respiratory depression is more likely to occur in elderly, cachectic, or debilitated patients because they may have altered pharmacokinetics or altered clearance compared to younger, healthier patients [see Warnings and Precautions (5.2)].

Regularly evaluate patients, particularly when initiating and titrating OTFC and when OTFC is given concomitantly with other drugs that depress respiration [see Warnings and Precautions (5.2), Drug Interactions (7)]. Alternatively, consider the use of non-opioid analgesics in these patients.

5.12 Adrenal Insufficiency

Cases of adrenal insufficiency have been reported with opioid use, more often following greater than one month of use. Presentation of adrenal insufficiency may include non-specific symptoms and signs including nausea, vomiting, anorexia, fatigue, weakness, dizziness, and low blood pressure. If adrenal insufficiency is suspected, confirm the diagnosis with diagnostic testing as soon as possible. If adrenal insufficiency is diagnosed, treat with physiologic replacement doses of corticosteroids. Wean the patient off of the opioid to allow adrenal function to recover and continue corticosteroid treatment until adrenal function recovers. Other opioids may be tried as some cases reported use of a different opioid without recurrence of adrenal insufficiency. The information available does not identify any particular opioids as being more likely to be associated with adrenal insufficiency.

5.13 Severe Hypotension

OTFC may cause severe hypotension including orthostatic hypotension and syncope in ambulatory patients. There is increased risk in patients whose ability to maintain blood pressure has already been compromised by a reduced blood volume or concurrent administration of certain CNS depressant drugs (e.g. phenothiazines or general anesthetics) [see Drug Interactions (7)]. Regularly evaluate these patients for signs of hypotension after initiating or titrating the dosage of OTFC. In patients with circulatory shock, OTFC may cause vasodilation that can further reduce cardiac output and blood pressure. Avoid the use of OTFC in patients with circulatory shock.

5.14 Risks of Use in Patients with Increased Intracranial Pressure, Brain Tumors, Head Injury, or Impaired Consciousness

In patients who may be susceptible to the intracranial effects of CO2 retention (e.g., those with evidence of increased intracranial pressure or brain tumors), OTFC may reduce respiratory drive, and the resultant CO2 retention can further increase intracranial pressure. Monitor such patients for signs of sedation and respiratory depression, particularly when initiating therapy with OTFC.

Opioids may also obscure the clinical course in a patient with a head injury. Avoid the use of OTFC in patients with impaired consciousness or coma.

5.15 Risks of Gastrointestinal Complications

OTFC is contraindicated in patients with known or suspected gastrointestinal obstruction, including paralytic ileus.

The fentanyl in OTFC may cause spasm of the sphincter of Oddi. Opioids may cause increases in serum amylase. Regularly evaluate patients with biliary tract disease, including acute pancreatitis for worsening symptoms.

Cases of opioid-induced esophageal dysfunction (OIED) have been reported in patients taking opioids. The risk of OIED may increase as the dose and/or duration of opioids increases. Regularly evaluate patients for signs and symptoms of OIED (e.g., dysphagia, regurgitation, non-cardiac chest pain) and, if necessary, adjust opioid therapy as clinically appropriate [see Clinical Pharmacology (12.2)].

5.16 Increased Risk of Seizures in Patients with Seizure Disorders

The fentanyl in OTFC may increase the frequency of seizures in patients with seizure disorders, and may increase the risk of seizures occurring in other clinical settings associated with seizures. Regularly evaluate patients with a history of seizure disorders for worsened seizure control during OTFC therapy.

5.17 Risks of Driving and Operating Machinery

OTFC may impair the mental or physical abilities needed to perform potentially hazardous activities such as driving a car or operating machinery. Warn patients not to drive or operate dangerous machinery unless they are tolerant to the effects of OTFC and know how they will react to the medication.

5.18 Cardiac Disease

Intravenous fentanyl may produce bradycardia. Therefore, use OTFC with caution in patients with bradyarrhythmias.

6 ADVERSE REACTIONS

The following serious adverse reactions are described, or described in greater detail, in other sections:

- Addiction, Abuse, and Misuse [see Warnings and Precautions (5.1)]
- Life-Threatening Respiratory Depression [see Warnings and Precautions (5.2)]
- Interactions with Benzodiazepines and Other CNS Depressants [see Warnings and Precautions (5.4)]
- Neonatal Opioid Withdrawal Syndrome [see Warnings and Precautions (5.8)]
- Opioid-Induced Hyperalgesia and Allodynia [see Warnings and Precautions (5.9)]
- Serotonin Syndrome [see Warnings and Precautions (5.10)]
- Adrenal Insufficiency [see Warnings and Precautions (5.12)]
- Severe Hypotension [see Warnings and Precautions (5.13)]
- Gastrointestinal Adverse Reactions [see Warnings and Precautions (5.15)]
- Seizures [see Warnings and Precautions (5.16)]

6.1 Clinical Studies Experience

Because clinical trials are conducted under widely varying conditions, adverse reaction rates observed in the clinical trials of a drug cannot be directly compared to rates in the clinical trials of another drug and may not reflect the rates observed in practice.

The safety of Oral Transmucosal Fentanyl Citrate (OTFC) has been evaluated in 257 opioid-tolerant chronic cancer pain patients. The duration of OTFC use varied during the open-label study. Some patients were followed for over 21 months. The average duration of therapy in the open-label study was 129 days.

The most serious adverse reactions associated with OTFC are respiratory depression (potentially leading to apnea or respiratory arrest), circulatory depression, hypotension, and shock.

Because the clinical trials of OTFC were designed to evaluate safety and efficacy in treating breakthrough cancer pain, all patients were also taking concomitant opioids, such as sustained-release morphine or transdermal fentanyl, for their persistent cancer pain. The adverse event data presented here reflect the actual percentage of patients experiencing each adverse effect among patients who received OTFC for breakthrough cancer pain along with a concomitant opioid for persistent cancer pain. There has been no attempt to correct for concomitant use of other opioids, duration of OTFC therapy, or cancer-related symptoms.

Three short-term clinical trials with similar titration schemes were conducted in 257 patients with malignancy and breakthrough cancer pain. Data are available for 254 of these patients. Table 1 lists, by dose groups, adverse reactions with an overall frequency of 1% or greater that occurred during titration. The ability to assign a dose-response relationship to these adverse reactions is limited by the titration schemes used in these studies. Adverse reactions are listed in descending order of frequency within each body system.

Table 1. Percent of Patients with Specific Adverse Events Commonly Associated with Opioid Administration or of Particular Clinical Interest Which Occurred During Titration (Events in 1% or More of Patients)
Dose Group |  | Percentage of Patients Reporting Event
Dose Group |  | 200-; 600 mcg; (n=230) | 800-; 1400 mcg (n=138) | 1600; mcg; (n=54) | >1600; mcg; (n=41) | Any; Dose [Any Dose = A patient who experienced the same adverse event at multiple doses was only counted once.]; (n=254)
Body As A Whole
 | Asthenia | 6 | 4 | 0 | 7 | 9
 | Headache | 3 | 4 | 6 | 5 | 6
 | Accidental Injury | 1 | 1 | 4 | 0 | 2
Digestive
 | Nausea | 14 | 15 | 11 | 22 | 23
 | Vomiting | 7 | 6 | 6 | 15 | 12
 | Constipation | 1 | 4 | 2 | 0 | 4
Nervous
 | Dizziness | 10 | 16 | 6 | 15 | 17
 | Somnolence | 9 | 9 | 11 | 20 | 17
 | Confusion | 1 | 6 | 2 | 0 | 4
 | Anxiety | 3 | 0 | 2 | 0 | 3
 | Abnormal Gait | 0 | 1 | 4 | 0 | 2
 | Dry Mouth | 1 | 1 | 2 | 0 | 2
 | Nervousness | 1 | 1 | 0 | 0 | 2
 | Vasodilatation | 2 | 0 | 2 | 0 | 2
 | Hallucinations | 0 | 1 | 2 | 2 | 1
 | Insomnia | 0 | 1 | 2 | 0 | 1
 | Thinking Abnormal | 0 | 1 | 2 | 0 | 1
 | Vertigo | 1 | 0 | 0 | 0 | 1
Respiratory
 | Dyspnea | 2 | 3 | 6 | 5 | 4
Skin
 | Pruritus | 1 | 0 | 0 | 5 | 2
 | Rash | 1 | 1 | 0 | 2 | 2
 | Sweating | 1 | 1 | 2 | 2 | 2
Special Senses
 | Abnormal Vision | 1 | 0 | 2 | 0 | 2

The following adverse reactions not reflected in Table 1 occurred during titration with an overall frequency of 1% or greater and are listed in descending order of frequency within each body system.

Body as a Whole: Pain, fever, abdominal pain, chills, back pain, chest pain, infection

Digestive: Diarrhea, dyspepsia, flatulence

Metabolic and Nutritional: Peripheral edema, dehydration

Nervous: Hypesthesia, migraine

Respiratory: Pharyngitis, cough increased

The following reactions occurred during titration with an overall frequency of less than 1% and are listed in descending order of frequency within each body system.

Body as a Whole: Bone pain

Cardiovascular: Deep thrombophlebitis, hypertension, hypotension

Digestive: Anorexia, eructation, fecal impaction, gum hemorrhage, mouth ulceration, oral moniliasis

Hemic and Lymphatic: Anemia, leukopenia

Metabolic and Nutritional: Edema, hypercalcemia, weight loss

Musculoskeletal: Myalgia, pathological fracture, myasthenia

Nervous: Abnormal dreams, urinary retention, agitation, amnesia, emotional lability, euphoria, incoordination, libido decreased, neuropathy, paresthesia, speech disorder

Respiratory: Hemoptysis, pleural effusion, rhinitis, asthma, hiccup, pneumonia, respiratory insufficiency, sputum increased

Skin and Appendages: Alopecia, exfoliative dermatitis

Special Senses: Taste perversion

Urogenital: Vaginal hemorrhage, dysuria, hematuria, urinary incontinence, urinary tract infection

A long-term extension study was conducted in 156 patients with malignancy and breakthrough cancer pain who were treated for an average of 129 days. Data are available for 152 of these patients. Table 2 lists by dose groups, adverse reactions with an overall frequency of 1% or greater that occurred during the long-term extension study. Adverse reactions are listed in descending order of frequency within each body system.

Table 2. Percent of Patients with Adverse Events Commonly Associated with Opioid Administration or of Particular Clinical Interest Which Occurred During Long Term Treatment (Events in 1% or More of Patients)
Dose Group |  | Percentage of Patients Reporting Event
Dose Group |  | 200-; 600 mcg; (n=98) | 800-; 1400 mcg; (n=83) | 1600; mcg; (n=53) | >1600; mcg; (n=27) | Any; Dose [Any Dose = A patient who experienced the same adverse event at multiple doses was only counted once.]; (n=152)
Body As A Whole
 | Asthenia | 25 | 30 | 17 | 15 | 38
 | Headache | 12 | 17 | 13 | 4 | 20
 | Accidental Injury | 4 | 6 | 4 | 7 | 9
 | Hypertonia | 2 | 2 | 2 | 0 | 3
Digestive
 | Nausea | 31 | 36 | 25 | 26 | 45
 | Vomiting | 21 | 28 | 15 | 7 | 31
 | Constipation | 14 | 11 | 13 | 4 | 20
 | Intestinal Obstruction | 0 | 2 | 4 | 0 | 3
Cardiovascular
 | Hypertension | 1 | 1 | 0 | 0 | 1
Nervous
 | Dizziness | 12 | 10 | 9 | 0 | 16
 | Anxiety | 9 | 8 | 8 | 7 | 15
 | Somnolence | 8 | 13 | 8 | 7 | 15
 | Confusion | 2 | 5 | 13 | 7 | 10
 | Depression | 9 | 4 | 2 | 7 | 9
 | Insomnia | 5 | 1 | 8 | 4 | 7
 | Abnormal Gait | 5 | 1 | 0 | 0 | 4
 | Dry Mouth | 3 | 1 | 2 | 4 | 4
 | Nervousness | 2 | 2 | 0 | 4 | 3
 | Stupor | 4 | 1 | 0 | 0 | 3
 | Vasodilatation | 1 | 1 | 4 | 0 | 3
 | Thinking Abnormal | 2 | 1 | 0 | 0 | 2
 | Abnormal Dreams | 1 | 1 | 0 | 0 | 1
 | Convulsion | 0 | 1 | 2 | 0 | 1
 | Myoclonus | 0 | 0 | 4 | 0 | 1
 | Tremor | 0 | 1 | 2 | 0 | 1
 | Vertigo | 0 | 0 | 4 | 0 | 1
Respiratory
 | Dyspnea | 15 | 16 | 8 | 7 | 22
Skin
 | Rash | 3 | 5 | 8 | 4 | 8
 | Sweating | 3 | 2 | 2 | 0 | 4
 | Pruritus | 2 | 0 | 2 | 0 | 2
Special Senses
 | Abnormal Vision | 2 | 2 | 0 | 0 | 3
Urogenital
 | Urinary Retention | 1 | 2 | 0 | 0 | 2

The following reactions not reflected in Table 2 occurred with an overall frequency of 1% or greater in the long-term extension study and are listed in descending order of frequency within each body system.

Body as a Whole: Pain, fever, back pain, abdominal pain, chest pain, flu syndrome, chills, infection, abdomen enlarged, bone pain, ascites, sepsis, neck pain, viral infection, fungal infection, cachexia, cellulitis, malaise, pelvic pain

Cardiovascular: Deep thrombophlebitis, palpitation, vascular disorder

Digestive: Diarrhea, anorexia, dyspepsia, dysphagia, oral moniliasis, mouth ulceration, rectal disorder, stomatitis, flatulence, gastrointestinal hemorrhage, gingivitis, jaundice, periodontal abscess, eructation, glossitis, rectal hemorrhage

Hemic and Lymphatic: Anemia, leukopenia, thrombocytopenia, ecchymosis, lymphadenopathy, lymphedema, pancytopenia

Metabolic and Nutritional: Peripheral edema, edema, dehydration, weight loss, hyperglycemia, hypokalemia, hypercalcemia, hypomagnesemia

Musculoskeletal: Myalgia, pathological fracture, joint disorder, leg cramps, arthralgia, bone disorder

Nervous: Hypesthesia, paresthesia, hypokinesia, neuropathy, speech disorder, migraine

Respiratory: Cough increased, pharyngitis, pneumonia, rhinitis, sinusitis, bronchitis, epistaxis, asthma, hemoptysis, sputum increased

Skin and Appendages: Skin ulcer, alopecia

Special Senses: Tinnitus, conjunctivitis, ear disorder, taste perversion

Urogenital: Urinary tract infection, urinary incontinence, breast pain, dysuria, hematuria, scrotal edema, hydronephrosis, kidney failure, urinary urgency, urination impaired, breast neoplasm, vaginal hemorrhage, vaginitis

The following reactions occurred with a frequency of less than 1% in the long-term extension study and are listed in descending order of frequency within each body system.

Body as a Whole: Allergic reaction, cyst, face edema, flank pain, granuloma, bacterial infection, mucous membrane disorder, neck rigidity

Cardiovascular: Angina pectoris, hemorrhage, hypotension, peripheral vascular disorder, postural hypotension, tachycardia

Digestive: Cheilitis, esophagitis, fecal incontinence, gastroenteritis, gastrointestinal disorder, gum hemorrhage, hemorrhage of colon, hepatorenal syndrome, liver tenderness, tooth caries, tooth disorder

Hemic and Lymphatic: Bleeding time increased

Metabolic and Nutritional: Acidosis, generalized edema, hypocalcemia, hypoglycemia, hyponatremia, hypoproteinemia, thirst

Musculoskeletal: Arthritis, muscle atrophy, myopathy, synovitis, tendon disorder

Nervous: Acute brain syndrome, agitation, cerebral ischemia, facial paralysis, foot drop, hallucinations, hemiplegia, miosis, subdural hematoma

Respiratory: Hiccup, hyperventilation, lung disorder, pneumothorax, respiratory failure, voice alteration

Skin and Appendages: Herpes zoster, maculopapular rash, skin discoloration, urticaria, vesiculobullous rash

Special Senses: Ear pain, eye hemorrhage, lacrimation disorder, partial permanent deafness, partial transitory deafness

Urogenital: Kidney pain, nocturia, oliguria, polyuria, pyelonephritis

6.2 Postmarketing Experience

The following adverse reactions have been identified during post approval use of OTFC. Because these reactions are reported voluntarily from a population of uncertain size, it is not always possible to reliably estimate their frequency or establish a causal relationship to drug exposure.

Digestive:

- Dental decay: Dental decay, including dental caries, tooth loss, and gum line erosion.

Nervous System Disorders:

- Serotonin syndrome: Cases of serotonin syndrome, a potentially life-threatening condition, have been reported during concomitant use of opioids with serotonergic drugs.

- Hyperalgesia and Allodynia: Cases of hyperalgesia and allodynia have been reported with opioid therapy of any duration [see Warnings and Precautions (5.9)].

Endocrine Disorders:

- Adrenal insufficiency: Cases of adrenal insufficiency have been reported with opioid use, more often following greater than one month of use.

- Androgen deficiency: Cases of androgen deficiency have occurred with use of opioids for an extended period of time [see Clinical Pharmacology (12.2)].

Immune System Disorders:

- Anaphylaxis: Anaphylaxis has been reported with ingredients contained in OTFC.

General Disorders and Administration Site Conditions:

- Application site reactions including irritation, pain, ulcer, and drug withdrawal syndrome.

Metabolic and Nutritional Disorders:

- Hypoglycemia: Cases of hypoglycemia have been reported in patients taking opioids. Most reports were in patients with at least one predisposing risk factor (e.g., diabetes).

Gastrointestinal Disorders:

- Opioid-induced esophageal dysfunction (OIED): Cases of OIED have been reported in patients taking opioids and may occur more frequently in patients taking higher doses of opioids, and/or in patients taking opioids longer term [see Warnings and Precautions (5.15)].

Adverse Reactions from Observational Studies

A prospective, observational cohort study estimated the risks of addiction, abuse, and misuse in patients initiating long-term use of Schedule II opioid analgesics between 2017 and 2021. Study participants included in one or more analyses had been enrolled in selected insurance plans or health systems for at least one year, were free of at least one outcome at baseline, completed a minimum number of follow-up assessments, and either: 1) filled multiple extended-release/long-acting opioid analgesic prescriptions during a 90-day period (n=978); or 2) filled any Schedule II opioid analgesic prescriptions covering at least 70 of 90 days (n=1,244). Those included also had no dispensing of the qualifying opioids in the previous 6 months.

Over 12 months:

- approximately 1% to 6% of participants across the two cohorts newly met criteria for addiction, as assessed with two validated interview-based measures of moderate-to-severe opioid use disorder based on Diagnostic and Statistical Manual of Mental Disorders, Fifth Edition (DSM-5) criteria, and
- approximately 9% and 22% of participants across the two cohorts newly met criteria for prescription opioid abuse and misuse [defined in Drug Abuse and Dependence (9.2)], respectively, as measured with a validated self-reported instrument.

A retrospective, observational cohort study estimated the risk of opioid-involved overdose or opioid overdose-related death in patients with new long-term use of Schedule II opioid analgesics from 2006 through 2016 (n=220,249). Included patients had been enrolled in either one of two commercial insurance programs, one managed care program, or one Medicaid program for at least 9 months. New long-term use was defined as having Schedule II opioid analgesic prescriptions covering at least 70 days’ supply over the 3 months prior to study entry and none during the preceding 6 months. Patients were excluded if they had an opioid-involved overdose in the 9 months prior to study entry. Overdose was measured using a validated medical code-based algorithm with linkage to the National Death Index database. The 5-year cumulative incidence estimates for opioid-involved overdose or opioid overdose-related death ranged from approximately 1.5% to 4% across study sites, counting only the first event during follow-up. Approximately 17% of first opioid overdoses observed over the entire study period (5-11 years, depending on the study site) were fatal. Higher baseline opioid dose was the strongest and most consistent predictor of opioid-involved overdose or opioid overdose-related death. Study exclusion criteria may have selected patients at lower risk of overdose, and substantial loss to follow-up (approximately 80%) also may have biased estimates.

The risk estimates from the studies described above may not be generalizable to all patients receiving opioid analgesics, such as those with exposures shorter or longer than the duration evaluated in the studies.

7 DRUG INTERACTIONS

Table 3 includes clinically significant drug interactions with Oral Transmucosal Fentanyl Citrate (OTFC).

Table 3: Clinically Significant Drug Interactions with OTFC
Inhibitors of CYP3A4
Clinical Impact: | The concomitant use of OTFC and CYP3A4 inhibitors can increase the plasma concentration of fentanyl, resulting in increased or prolonged opioid effects, particularly when an inhibitor is added after a stable dose of OTFC is achieved [see Warnings and Precautions (5.6)].; After stopping a CYP3A4 inhibitor, as the effects of the inhibitor decline, the fentanyl plasma concentration will decrease [see Clinical Pharmacology (12.3)], resulting in decreased opioid efficacy or a withdrawal syndrome in patients who had developed physical dependence to fentanyl.
Intervention: | If concomitant use is necessary, consider dosage reduction of OTFC until stable drug effects are achieved. Evaluate patients at frequent intervals for respiratory depression and sedation. If a CYP3A4 inhibitor is discontinued, consider increasing the OTFC dosage until stable drug effects are achieved. Evaluate for signs of opioid withdrawal.
Examples: | Macrolide antibiotics (e.g., erythromycin), azole-antifungal agents (e.g., ketoconazole), protease inhibitors (e.g., ritonavir), grapefruit juice
CYP3A4 Inducers
Clinical Impact: | The concomitant use of OTFC and CYP3A4 inducers can decrease the plasma concentration of fentanyl [see Clinical Pharmacology (12.3)], resulting in decreased efficacy or onset of a withdrawal syndrome in patients who have developed physical dependence to fentanyl [see Warnings and Precautions (5.6)].; After stopping a CYP3A4 inducer, as the effects of the inducer decline, the fentanyl plasma concentration will increase [see Clinical Pharmacology (12.3)], which could increase or prolong both the therapeutic effects and adverse reactions, and may cause serious respiratory depression.
Intervention: | If concomitant use is necessary, consider increasing the OTFC dosage until stable drug effects are achieved. Evaluate for signs of opioid withdrawal. If a CYP3A4 inducer is discontinued, consider OTFC dosage reduction and evaluate patients at frequent intervals for signs of respiratory depression and sedation.
Examples: | Rifampin, carbamazepine, phenytoin
Benzodiazepines and Other Central Nervous System (CNS) Depressants
Clinical Impact: | Due to additive pharmacologic effect, the concomitant use of benzodiazepines or other CNS depressants including alcohol, increases the risk of respiratory depression, profound sedation, coma, and death.
Intervention: | Reserve concomitant prescribing of these drugs for use in patients for whom alternative treatment options are inadequate. Limit dosages and durations to the minimum required. Inform patients and caregivers of this potential interaction and educate them on the signs and symptoms of respiratory depression (including sedation). If concomitant use is warranted, consider recommending or prescribing an opioid overdose reversal agent [see Dosage and Administration (2.2), Warnings and Precautions (5.1, 5.2, 5.4)].
Examples: | Benzodiazepines and other sedatives/hypnotics, anxiolytics, tranquilizers, muscle relaxants, general anesthetics, antipsychotics, gabapentinoids (gabapentin or pregabalin), other opioids, alcohol.
Serotonergic Drugs
Clinical Impact: | The concomitant use of opioids with other drugs that affect the serotonergic neurotransmitter system has resulted in serotonin syndrome [see Warnings and Precautions (5.10)].
Intervention: | If concomitant use is warranted, frequently evaluate the patient, particularly during treatment initiation and dose adjustment. Discontinue OTFC if serotonin syndrome is suspected.
Examples: | Selective serotonin reuptake inhibitors (SSRIs), serotonin and norepinephrine reuptake inhibitors (SNRIs), tricyclic antidepressants (TCAs), triptans, 5-HT3 receptor antagonists, drugs that affect the serotonin neurotransmitter system (e.g., mirtazapine, trazodone, tramadol), certain muscle relaxants (i.e., cyclobenzaprine, metaxalone), monoamine oxidase (MAO) inhibitors (those intended to treat psychiatric disorders and also others, such as linezolid and intravenous methylene blue).
Monoamine Oxidase Inhibitors (MAOIs)
Clinical Impact: | MAOI interactions with opioids may manifest as serotonin syndrome [see Warnings and Precautions (5.10)] or opioid toxicity (e.g., respiratory depression, coma) [see Warnings and Precautions (5.2)].
Intervention: | The use of OTFC is not recommended for patients taking MAOIs or within 14 days of stopping such treatment.
Examples: | Phenelzine, tranylcypromine, linezolid
Mixed Agonist/Antagonist and Partial Agonist Opioid Analgesics
Clinical Impact: | May reduce the analgesic effect of OTFC and/or precipitate withdrawal symptoms.
Intervention: | Avoid concomitant use.
Examples: | Butorphanol, nalbuphine, pentazocine, buprenorphine
Muscle Relaxants
Clinical Impact: | Fentanyl may enhance the neuromuscular blocking action of skeletal muscle relaxants and produce an increased degree of respiratory depression.
Intervention: | Because respiratory depression may be greater than otherwise expected, decrease the dosage of OTFC and/or the muscle relaxant as necessary. Due to the risk of respiratory depression with concomitant use of skeletal muscle relaxants and opioids, consider recommending or prescribing an opioid overdose reversal agent [see Dosage and Administration (2.2), Warnings and Precautions (5.2, 5.4)].
Examples: | Cyclobenzaprine, metaxalone
Diuretics
Clinical Impact: | Opioids can reduce the efficacy of diuretics by inducing the release of antidiuretic hormone.
Intervention: | Evaluate patients for signs of diminished diuresis and/or effects on blood pressure and increase the dosage of the diuretic as needed.
Anticholinergic Drugs
Clinical Impact: | The concomitant use of anticholinergic drugs may increase risk of urinary retention and/or severe constipation, which may lead to paralytic ileus.
Intervention: | Evaluate patients for signs of urinary retention or reduced gastric motility when OTFC is used concomitantly with anticholinergic drugs.

8 USE IN SPECIFIC POPULATIONS

8.1 Pregnancy

Risk Summary

Use of opioid analgesics for an extended period of time during pregnancy may cause neonatal opioid withdrawal syndrome [see Warnings and Precautions (5.8)]. Available data with Oral Transmucosal Fentanyl Citrate (OTFC) in pregnant women are insufficient to inform a drug-associated risk for major birth defects and miscarriage. There are risks to the mother and infant associated with use of OTFC for an extended period of time during pregnancy (see Clinical Considerations).

In animal reproduction studies, fentanyl administration to pregnant rats during organogenesis was embryocidal at doses within the range of the human recommended dosing. When administered during gestation through lactation fentanyl administration to pregnant rats resulted in reduced pup survival at doses within the range of the human recommended dosing. No evidence of malformations were noted in animal studies completed to date [see Data].

The background risk of major birth defects and miscarriage for the indicated population is unknown. All pregnancies have a background risk of birth defect, loss, or other adverse outcomes. In the U.S. general population, the estimated background risk of major birth defects and miscarriage in clinically recognized pregnancies is 2 to 4% and 15 to 20%, respectively.

Clinical Considerations

Fetal/Neonatal Adverse Reactions

Use of opioid analgesics for an extended period of time during pregnancy for medical or nonmedical purposes can result in physical dependence in the neonate and neonatal opioid withdrawal syndrome shortly after birth.

Neonatal opioid withdrawal syndrome presents as irritability, hyperactivity and abnormal sleep pattern, high pitched cry, tremor, vomiting, diarrhea, and failure to gain weight. The onset of neonatal withdrawal symptoms usually occurs in the first days after birth. The duration and severity of neonatal opioid withdrawal syndrome may vary. Observe newborns for symptoms of neonatal opioid withdrawal syndrome and manage accordingly [see Warnings and Precautions (5.8)].

Labor or Delivery

Opioids cross the placenta and may produce respiratory depression and psycho-physiologic effects in neonates. An opioid overdose reversal agent, such as naloxone or nalmefene, must be available for reversal of opioid-induced respiratory depression in the neonate. OTFC is not recommended for use in pregnant women during or immediately prior to labor, when other analgesic techniques are more appropriate. Opioid analgesics, including OTFC, can prolong labor through actions which temporarily reduce the strength, duration, and frequency of uterine contractions. However, this effect is not consistent and may be offset by an increased rate of cervical dilation, which tends to shorten labor. Monitor neonates exposed to opioid analgesics during labor for signs of excess sedation and respiratory depression.

Data

Human Data

In women treated acutely with intravenous or epidural fentanyl during labor, symptoms of neonatal respiratory or neurological depression were no more frequent than would be expected in infants of untreated mothers.

Transient neonatal muscular rigidity has been observed in infants whose mothers were treated with intravenous fentanyl.

Animal Data

Fentanyl (25, 50, or 100 mcg/kg) citrate was administered subcutaneously to pregnant rats during the period of organogenesis (Gestation Day, GD 6 to 17). Maternal toxicity and a decrease in fetal weights were observed at 100 mcg/kg but no teratogenicity was seen in the study (the no observed effect level of 50 mcg/kg is equivalent to 0.7 times the exposure of a single human dose of 1600 mcg per pain episode, based on an AUC comparison). Fentanyl (50, 100, or 250 mcg/kg) was also administered subcutaneously to pregnant rabbits during the period of organogenesis (GD 6-18). Maternal toxicity was noted at doses >100 mcg/kg. No teratogenicity was seen in the study (250 mcg/kg dose is equivalent to 3.5 times the exposure of a single human dose of 1600 mcg per pain episode, based on an AUC comparison).

Fentanyl has been shown to be embryocidal in pregnant rats at doses of 30 mcg/kg intravenously (0.2 times the 1600 mcg dose of OTFC on a mg/m^2 basis) from GD 6 to 18 and 160 mcg/kg subcutaneously (1 times the 1600 mcg dose of OTFC based on a mg/m^2 basis). No evidence of teratogenicity was reported.

No evidence of malformations or adverse effects on the fetus was reported in a published study in which pregnant rats were administered fentanyl continuously via subcutaneously implanted osmotic minipumps at doses of 10, 100, or 500 mcg/kg/day starting 2-weeks prior to breeding and throughout pregnancy. The high dose was approximately 3 times the human dose of 1600 mcg OTFC per pain episode on a mg/m^2 basis and produced mean steady-state plasma levels that are 3.4 times higher than the mean Cmax observed following administration of 1600 mcg dose of OTFC in humans.

In a postnatal development study, pregnant rats were treated from GD 6 through Lactation Day (LD) 20 with subcutaneous doses of fentanyl (25, 50, 100, and 400 mcg/kg). Maternal toxicity was noted at doses >100 mcg/kg. A reduction in pup growth and delayed attainment of developmental indices were observed at >100 mcg/kg. No difference in the number of live pups/litter was seen at birth, however, pup survival at LD 4 was reduced to 48% at 400 mcg/kg and by LD 21 pup survival was reduced to 30% and 26% at 100 and 400 mcg/kg, respectively. During lactation, fentanyl-related clinical signs (decreased activity, skin cold to touch, and moribund appearance) were noted in the F1 pups, most prominently in the 400 mcg/kg group. Pups from this group also had significantly reduced body weights throughout the lactation period. The dose of fentanyl administered to rats at which no developmental toxicity in the F1 generation was seen was 50 mcg/kg which is 0.6 times the exposure of a single human dose of 1600 mcg per pain episode, based on an AUC comparison.

8.2 Lactation

Risk Summary

Fentanyl is present in breast milk. One published lactation study reports a relative infant dose of fentanyl of 0.024%. However, there is insufficient information to determine the effects of fentanyl on the breastfed infant and the effects of fentanyl on milk production. Because of the potential for serious adverse reactions, including excess sedation and respiratory depression in a breastfed infant, advise patients that breastfeeding is not recommended during treatment with OTFC.

Clinical Considerations

Monitor infants exposed to OTFC through breast milk for excess sedation and respiratory depression. Withdrawal symptoms can occur in breastfed infants when maternal administration of an opioid analgesic is stopped, or when breastfeeding is stopped.

8.3 Females and Males of Reproductive Potential

Infertility

Use of opioids for an extended period of time may cause reduced fertility in females and males of reproductive potential. It is not known whether these effects on fertility are reversible [see Adverse Reactions (6.2), Clinical Pharmacology (12.2), Nonclinical Toxicology (13.1)].

8.4 Pediatric Use

Safety and effectiveness in pediatric patients below 16 years of age have not been established.

In a clinical study, 15 opioid-tolerant pediatric patients with breakthrough pain, ranging in age from 5 to 15 years, were treated with OTFC. The study was too small to allow conclusions on safety and efficacy in this patient population. Twelve of the fifteen opioid-tolerant children and adolescents aged 5 to 15 years in this study received OTFC at doses ranging from 200 mcg to 600 mcg. The mean (CV%; range) dose-normalized (to 200 mcg) Cmax and AUC0-8 values were 0.87 ng/mL (51%; 0.42-1.30) and 4.54 ng.h/mL (42%; 2.37-6.0), respectively, for children ages 5 to <11 years old (N = 3) and 0.68 ng/mL (72%; 0.15-1.44) and 8.38 (192%; 0.84-50.78), respectively, for children ages ≥11 to <16 y (N = 9).

8.5 Geriatric Use

Of the 257 patients in clinical studies of OTFC in breakthrough cancer pain, 61 (24%) were 65 years of age and older, while 15 (6%) were 75 years of age and older. Those patients over the age of 65 years were titrated to a mean dose that was about 200 mcg less than the mean dose titrated to by younger patients. No difference was noted in the safety profile of the group over 65 years of age as compared to younger patients in OTFC clinical trials.

Elderly patients have been shown to be more sensitive to the effects of fentanyl when administered intravenously, compared with the younger population. Therefore, exercise caution when individually titrating OTFC in elderly patients to provide adequate efficacy while minimizing risk.

Respiratory depression is the chief risk for elderly patients treated with opioids, and has occurred after large initial doses were administered to patients who were not opioid-tolerant or when opioids were co-administered with other agents that depress respiration. Titrate the dosage of OTFC slowly in geriatric patients and frequently reevaluate the patient for signs of central nervous system and respiratory depression [see Warnings and Precautions (5.11)].

Fentanyl is known to be substantially excreted by the kidney, and the risk of adverse reactions to this drug may be greater in patients with impaired renal function. Because elderly patients are more likely to have decreased renal function, care should be taken in dose selection, and it may be useful to regularly evaluate renal function.

8.6 Patients with Renal or Hepatic Impairment

Insufficient information exists to make recommendations regarding the use of OTFC in patients with impaired renal or hepatic function. Fentanyl is metabolized primarily via human cytochrome P450 3A4 isoenzyme system and mostly eliminated in urine. If the drug is used in these patients, it should be used with caution because of the hepatic metabolism and renal excretion of fentanyl.

8.7 Sex

Both male and female opioid-tolerant patients with cancer were studied for the treatment of breakthrough cancer pain. No clinically relevant sex differences were noted either in dosage requirement or in observed adverse reactions.

9 DRUG ABUSE AND DEPENDENCE

9.1 Controlled Substance

Oral Transmucosal Fentanyl Citrate (OTFC) contains fentanyl, a Schedule II controlled substance.

9.2 Abuse

OTFC contains fentanyl, a substance with high potential for misuse and abuse, which can lead to the development of substance use disorder, including addiction [see Warnings and Precautions (5.1)].

Misuse is the intentional use, for therapeutic purposes, of a drug by an individual in a way other than prescribed by a healthcare provider or for whom it was not prescribed.

Abuse is the intentional, non-therapeutic use of a drug, even once, for its desirable psychological or physiological effects.

Drug addiction is a cluster of behavioral, cognitive, and physiological phenomena that may include a strong desire to take the drug, difficulties in controlling drug use (e.g., continuing drug use despite harmful consequences, giving a higher priority to drug use than other activities and obligations), and possible tolerance or physical dependence.

Misuse and abuse of OTFC increases risk of overdose, which may lead to central nervous system and respiratory depression, hypotension, seizures, and death. The risk is increased with concurrent abuse of OTFC with alcohol and/or other CNS depressants. Abuse of and addiction to opioids in some individuals may not be accompanied by concurrent tolerance and symptoms of physical dependence. In addition, abuse of opioids can occur in the absence of addiction.

All patients treated with opioids require careful and frequent reevaluation for signs of misuse, abuse, and addiction, because use of opioid analgesic products carries the risk of addiction even under appropriate medical use. Patients at high risk of OTFC abuse include those with a history of prolonged use of any opioid, including products containing fentanyl, those with a history of drug or alcohol abuse, or those who use OTFC in combination with other abused drugs.

“Drug-seeking” behavior is very common in persons with substance use disorders. Drug-seeking tactics include emergency calls or visits near the end of office hours, refusal to undergo appropriate examination, testing, or referral, repeated “loss” of prescriptions, tampering with prescriptions, and reluctance to provide prior medical records or contact information for other treating healthcare provider(s). “Doctor shopping” (visiting multiple prescribers to obtain additional prescriptions) is common among people who abuse drugs and people with substance use disorder. Preoccupation with achieving adequate pain relief can be appropriate behavior in a patient with inadequate pain control.

OTFC, like other opioids, can be diverted for nonmedical use into illicit channels of distribution. Careful record-keeping of prescribing information, including quantity, frequency, and renewal requests, as required by state and federal law, is strongly advised.

Proper assessment of the patient, proper prescribing practices, periodic reevaluation of therapy, and proper dispensing and storage are appropriate measures that help to limit abuse of opioid drugs.

Risks Specific to Abuse of OTFC

Abuse of OTFC poses a risk of overdose and death. The risk is increased with concurrent use of OTFC with alcohol and/or other CNS depressants.

OTFC is approved for oral transmucosal use only.

9.3 Dependence

Both tolerance and physical dependence can develop during use of opioid therapy.

Tolerance is a physiological state characterized by a reduced response to a drug after repeated administration (i.e., a higher dose of a drug is required to produce the same effect that was once obtained at a lower dose).

Physical dependence is a state that develops as a result of a physiological adaptation in response to repeated drug use, manifested by withdrawal signs and symptoms after abrupt discontinuation or a significant dose reduction of a drug.

Withdrawal may be precipitated through the administration of drugs with opioid antagonist activity (e.g., naloxone, nalmefene), mixed agonist/antagonist analgesics (e.g., pentazocine, butorphanol, nalbuphine), or partial agonists (e.g., buprenorphine). Physical dependence may not occur to a clinically significant degree until after several days to weeks of continued use.

Infants born to mothers physically dependent on opioids will also be physically dependent and may exhibit respiratory difficulties and withdrawal signs [see Use in Specific Populations (8.1)].

10 OVERDOSAGE

Clinical Presentation

Acute overdose with fentanyl can be manifested by respiratory depression, somnolence progressing to stupor or coma, skeletal muscle flaccidity, cold and clammy skin, constricted pupils, and, in some cases, pulmonary edema, bradycardia, hypotension, hypoglycemia, partial or complete airway obstruction, atypical snoring, and death. Marked mydriasis rather than miosis may be seen with hypoxia in overdose situations [see Clinical Pharmacology (12.2)]. Toxic leukoencephalopathy has been reported after opioid overdose and can present hours, days, or weeks after apparent recovery from the initial intoxication.

Treatment of Overdose

In case of overdose, priorities are: removal of the OTFC unit, if still in the mouth, the reestablishment of a patent and protected airway and institution of assisted or controlled ventilation, if needed. Employ other supportive measures (including oxygen and vasopressors) in the management of circulatory shock and pulmonary edema as indicated. Cardiac arrest or arrhythmias will require advanced life-support measures.

For clinically significant respiratory or circulatory depression secondary to opioid overdose, administer an opioid overdose reversal agent such as naloxone or nalmefene.

Because the duration of opioid reversal is expected to be less than the duration of action of fentanyl in OTFC, carefully monitor the patient until spontaneous respiration is reliably re-established. If the response to an opioid overdose reversal agent is suboptimal or only brief in nature, administer additional reversal agent as directed by the product’s prescribing information.

In an individual physically dependent on opioids, administration of the recommended usual dosage of the opioid overdose reversal agent will precipitate an acute withdrawal syndrome. The severity of the withdrawal symptoms experienced will depend on the degree of physical dependence and the dose of the reversal agent administered. If a decision is made to treat serious respiratory depression in the physically dependent patient, administration of the reversal agent should be initiated with care and by titration with smaller than usual doses of the reversal agent.

11 DESCRIPTION

Oral Transmucosal Fentanyl Citrate (OTFC) (fentanyl citrate) oral transmucosal lozenge is a solid formulation of fentanyl, an opioid agonist, intended for oral transmucosal administration. OTFC is formulated as a white to off-white solid drug matrix on a handle that is fracture resistant (ABS plastic) under normal conditions when used as directed.

OTFC is designed to be dissolved slowly in the mouth to facilitate transmucosal absorption. The handle allows the OTFC unit to be removed from the mouth if signs of excessive opioid effects appear during administration.

Active Ingredient: Fentanyl citrate, USP is N-(1-Phenethyl-4-piperidyl) propionanilide citrate (1:1). Fentanyl is a highly lipophilic compound (octanol-water partition coefficient at pH 7.4 is 816:1) that is freely soluble in organic solvents and sparingly soluble in water (1:40). The molecular weight of the free base is 336.5 (the citrate salt is 528.6). The pKa of the tertiary nitrogens are 7.3 and 8.4. The compound has the following structural formula:

Inactive Ingredients: Hydrated dextrates, citric acid, dibasic sodium phosphate, artificial berry flavor, magnesium stearate, and edible glue (modified food starch and confectioner’s sugar).

12 CLINICAL PHARMACOLOGY

12.1 Mechanism of Action

Fentanyl is an opioid agonist whose principal therapeutic action is analgesia.

12.2 Pharmacodynamics

Effects on the Central Nervous System

The precise mechanism of the analgesic action is unknown although fentanyl is known to be a mu-opioid receptor agonist. Specific CNS opioid receptors for endogenous compounds with opioid-like activity have been identified throughout the brain and spinal cord and play a role in the analgesic effects of this drug.

Fentanyl produces respiratory depression by direct action on brain stem respiratory centers. The respiratory depression involves a reduction in the responsiveness of the brain stem to both increases in carbon dioxide and electrical stimulation.

Fentanyl causes miosis even in total darkness. Pinpoint pupils are a sign of opioid overdose but are not pathognomonic (e.g., pontine lesions of hemorrhagic or ischemic origin may produce similar findings). Marked mydriasis rather than miosis may be seen due to hypoxia in overdose situations.

Effects on the Gastrointestinal Tract and Other Smooth Muscle

Fentanyl causes a reduction in motility associated with an increase in smooth muscle tone in the antrum of the stomach and in the duodenum. Digestion of food in the small intestine is delayed and propulsive contractions are decreased. Propulsive peristaltic waves in the colon are decreased, while tone may be increased to the point of spasm resulting in constipation. Other opioid-induced effects may include a reduction in biliary and pancreatic secretions, spasm of the sphincter of Oddi, transient elevations in serum amylase, and opioid-induced esophageal dysfunction (OIED).

Effects on the Cardiovascular System

Fentanyl may produce release of histamine with or without associated peripheral vasodilation. Fentanyl produces peripheral vasodilation which may result in orthostatic hypotension or syncope. Manifestations of histamine release and/or peripheral vasodilation may include pruritus, flushing, red eyes, and sweating, and/or orthostatic hypotension.

Effects on the Endocrine System

Opioids inhibit the secretion of adrenocorticotropic hormone (ACTH), cortisol, and luteinizing hormone (LH) in humans [see Adverse Reactions (6.2)]. They also stimulate prolactin, growth hormone (GH) secretion, and pancreatic secretion of insulin and glucagon [see Adverse Reactions (6.2)]. Thyroid stimulating hormone (TSH) has been shown to be both inhibited and stimulated by opioids.

Use of opioids for an extended period of time may influence the hypothalamic-pituitary-gonadal axis, leading to androgen deficiency that may manifest as low libido, impotence, erectile dysfunction, amenorrhea, or infertility. The causal role of opioids in the clinical syndrome of hypogonadism is unknown because the various medical, physical, lifestyle, and psychological stressors that may influence gonadal hormone levels have not been adequately controlled for in studies conducted to date [see Adverse Reactions (6.2)].

Effects on the Immune System

Opioids have been shown to have a variety of effects on components of the immune system in in vitro and animal models. The clinical significance of these findings is unknown. Overall, the effects of opioids appear to be modestly immunosuppressive.

Concentration-Efficacy Relationships

The analgesic effects of fentanyl are related to the blood level of the drug, if proper allowance is made for the delay into and out of the CNS (a process with a 3- to 5-minute half-life).

In general, the effective concentration and the concentration at which toxicity occurs increase with increasing tolerance with any and all opioids. The rate of development of tolerance varies widely among individuals.

The minimum effective analgesic concentration of fentanyl for any individual patient may increase over time due to an increase in pain, the development of a new pain syndrome and/or the development of analgesic tolerance.

Concentration-Adverse Reaction Relationships

There is a relationship between increasing fentanyl plasma concentration and increasing frequency of dose-related opioid adverse reactions such as nausea, vomiting, CNS effects, and respiratory depression. In opioid-tolerant patients, the situation may be altered by the development of tolerance to opioid-related adverse reactions [see Dosage and Administration (2.1, 2.3, 2.4, 2.5)].

Respiratory System

All opioid mu-receptor agonists, including fentanyl, produce dose-dependent respiratory depression. The risk of respiratory depression is less in patients receiving chronic opioid therapy who develop tolerance to respiratory depression and other opioid effects. During the titration phase of the clinical trials, somnolence, which may be a precursor to respiratory depression, did increase in patients who were treated with higher doses of Oral Transmucosal Fentanyl Citrate (OTFC). Peak respiratory depressive effects may be seen as early as 15 to 30 minutes from the start of oral transmucosal fentanyl citrate product administration and may persist for several hours.

Serious or fatal respiratory depression can occur even at recommended doses. Although not observed with oral transmucosal fentanyl products in clinical trials, fentanyl given rapidly by intravenous injection in large doses may interfere with respiration by causing rigidity in the muscles of respiration [see Warnings and Precautions (5), Overdosage (10)].

12.3 Pharmacokinetics

Absorption

The absorption pharmacokinetics of fentanyl from the oral transmucosal dosage form is a combination of an initial rapid absorption from the buccal mucosa and a more prolonged absorption of swallowed fentanyl from the GI tract. Both the blood fentanyl profile and the bioavailability of fentanyl will vary depending on the fraction of the dose that is absorbed through the oral mucosa and the fraction swallowed.

Absolute bioavailability, as determined by area under the concentration-time curve, of 15 mcg/kg in 12 adult males was 50% compared to intravenous fentanyl.

Normally, approximately 25% of the total dose of OTFC is rapidly absorbed from the buccal mucosa and becomes systemically available. The remaining 75% of the total dose is swallowed with the saliva and then is slowly absorbed from the GI tract. About 1/3 of this amount (25% of the total dose) escapes hepatic and intestinal first-pass elimination and becomes systemically available. Thus, the generally observed 50% bioavailability of OTFC is divided equally between rapid transmucosal and slower GI absorption. Therefore, a unit dose of OTFC, if chewed and swallowed, might result in lower peak concentrations and lower bioavailability than when consumed as directed.

Dose proportionality among four of the available strengths of OTFC (200, 400, 800, and 1600 mcg) has been demonstrated in a balanced crossover design in adult subjects (n=11). Mean serum fentanyl levels following these four doses of OTFC are shown in Figure 1. The curves for each dose level are similar in shape with increasing dose levels producing increasing serum fentanyl levels. Cmax and AUC0→∞ increased in a dose-dependent manner that is approximately proportional to the OTFC administered.

Figure 1. Mean Serum Fentanyl Concentration (ng/mL) in Adult Subjects Comparing 4 Doses of OTFC

The pharmacokinetic parameters of the four strengths of OTFC tested in the dose-proportionality study are shown in Table 4. The mean Cmax ranged from 0.39 - 2.51 ng/mL. The median time of maximum plasma concentration (Tmax) across these four doses of OTFC varied from 20 - 40 minutes (range of 20 – 480 minutes) as measured after the start of administration.

Table 4. Pharmacokinetic Parameters* in Adult Subjects Receiving 200, 400, 800, and 1600 mcg Units of OTFC
Pharmacokinetic Parameter | 200 mcg | 400 mcg | 800 mcg | 1600 mcg
Tmax, minute median (range) | 40 (20-120) | 25 (20-240) | 25 (20-120) | 20 (20-480)
Cmax, ng/mL mean (%CV) | 0.39 (23) | 0.75 (33) | 1.55 (30) | 2.51 (23)
AUC0-1440, ng/mL minute; mean (%CV) | 102 (65) | 243 (67) | 573 (64) | 1026 (67)
t1/2, minute; mean (%CV) | 193 (48) | 386 (115) | 381 (55) | 358 (45)
* Based on arterial blood samples.

Distribution

Fentanyl is highly lipophilic. Animal data showed that following absorption, fentanyl is rapidly distributed to the brain, heart, lungs, kidneys and spleen followed by a slower redistribution to muscles and fat. The plasma protein binding of fentanyl is 80-85%. The main binding protein is alpha-1-acid glycoprotein, but both albumin and lipoproteins contribute to some extent. The free fraction of fentanyl increases with acidosis. The mean volume of distribution at steady state (Vss) was 4 L/kg.

Elimination

The total plasma clearance of fentanyl was 0.5 L/hr/kg (range 0.3 – 0.7 L/hr/kg). The terminal elimination half-life after OTFC administration is about 7 hours.

Metabolism

Fentanyl is metabolized in the liver and in the intestinal mucosa to norfentanyl by cytochrome P450 3A4 isoform. Norfentanyl was not found to be pharmacologically active in animal studies [see Drug Interactions (7)].

Excretion

Fentanyl is primarily (more than 90%) eliminated by biotransformation to N-dealkylated and hydroxylated inactive metabolites. Less than 7% of the dose is excreted unchanged in the urine, and only about 1% is excreted unchanged in the feces. The metabolites are mainly excreted in the urine, while fecal excretion is less important.

13 NONCLINICAL TOXICOLOGY

13.1 Carcinogenesis, Mutagenesis, Impairment of Fertility

Carcinogenesis

Fentanyl was evaluated for carcinogenic potential in a 104-week rat study and in a 6-month Tg.AC transgenic mouse study. In rats, doses up to 50 mcg/kg in males and 100 mcg/kg in females were administered subcutaneously and no treatment-related neoplasms were observed (doses are equivalent to 1.13 and 2.7 times the exposure of a single human dose of 1600 mcg per pain episode, respectively, based on an AUC comparison). In a 26-week transgenic mice model (Tg.AC), at topical doses up to 50 mcg/dose/day, no increase in the occurrence of treatment-related neoplasms was observed.

Mutagenesis

Fentanyl citrate was not mutagenic in the in vitro Ames reverse mutation assay in S. typhimurium or E. coli, or the mouse lymphoma mutagenesis assay, and was not clastogenic in the in vivo mouse micronucleus assay.

Impairment of Fertility

In a fertility study, female rats were administered fentanyl subcutaneously for 14 days prior to mating with untreated males at doses up to 300 mcg/kg and no effects on female fertility were observed. The systemic exposure at the dose of 300 mcg/kg was approximately 4.0-times the exposure of a single human dose of 1600 mcg per pain episode, based on an AUC comparison. Males were administered fentanyl subcutaneously for 28 days prior to mating with untreated females at doses up to 300 mcg/kg. At 300 mcg/kg, adverse effects on sperm parameters, which affected fertility, were observed. These effects included decreased percent mobile sperm, decreased sperm concentrations as well as an increase in the percent abnormal sperm. The dose in males at which no effects on fertility were observed was 100 mcg/kg, which is approximately 2.7 times the exposure of a single human dose of 1600 mcg per pain episode, based on an AUC comparison.

Fentanyl has been shown to impair fertility in rats at doses of 30 mcg/kg IV and 160 mcg/kg subcutaneously. Conversion to the human equivalent doses indicates that this is within the range of the human recommended dosing for OTFC.

14 CLINICAL STUDIES

Oral Transmucosal Fentanyl Citrate (OTFC) was investigated in clinical trials involving 257 opioid tolerant adult cancer patients experiencing breakthrough cancer pain. Breakthrough cancer pain was defined as a transient flare of moderate-to-severe pain occurring in cancer patients experiencing persistent cancer pain otherwise controlled with maintenance doses of opioid medications including at least 60 mg morphine/day, 50 mcg transdermal fentanyl/hour, or an equianalgesic dose of another opioid for a week or longer.

In two dose titration studies 95 of 127 patients (75%) who were on stable doses of either long-acting oral opioids or transdermal fentanyl for their persistent cancer pain titrated to a successful dose of OTFC to treat their breakthrough cancer pain within the dose range offered (200, 400, 600, 800, 1200, and 1600 mcg). A “successful” dose was defined as a dose where one unit of OTFC could be used consistently for at least two consecutive days to treat breakthrough cancer pain without unacceptable side effects. In these studies 11% of patients withdrew due to adverse reactions and 14% withdrew due to other reasons.

The successful dose of OTFC for breakthrough cancer pain was not predicted from the daily maintenance dose of opioid used to manage the persistent cancer pain and is thus best determined by dose titration.

A double-blind placebo controlled crossover study was performed in cancer patients to evaluate the effectiveness of OTFC for the treatment of breakthrough cancer pain. Of 130 patients who entered the study 92 patients (71%) achieved a successful dose during the titration phase. The distribution of successful doses is shown in Table 5.

Table 5. Successful Dose of OTFC Following Initial Titration
OTFC Dose | Total No. (%); (N=92)
200 mcg | 13 (14)
400 mcg | 19 (21)
600 mcg | 14 (15)
800 mcg | 18 (20)
1200 mcg | 13 (14)
1600 mcg | 15 (16)
Mean +/- SD | 789 +/- 468 mcg

On average, patients over 65 years of age titrated to a mean dose that was about 200 mcg less than the mean dose to which younger adult patients were titrated.

OTFC was administered beginning at Time 0 minutes and produced more pain relief compared with placebo at 15, 30, 45, and 60 minutes as measured after the start of administration (see Figure 2). The differences were statistically significant.

Figure 2. Pain Relief (PR) Scores (Mean±SD) During the Double-Blind Phase – All Patients with Evaluable Episodes on Both OTFC and Placebo (N=86)

^1 0 minutes = Start of administration of OTFC

^2 15 minutes = First time to measure pain relief

16 HOW SUPPLIED/STORAGE AND HANDLING

Oral Transmucosal Fentanyl Citrate (OTFC) is supplied in six dosage strengths. Each unit is individually wrapped in a child-resistant, protective blister package. These blister packages are packed 30 per shelf carton for use when patients have been titrated to the appropriate dose.

Each dosage unit has a white to off-white color. Each individual solid drug matrix is marked with “FENTANYL” and the strength of the unit (“200”, “400”, “600”, “800”, “1200”, or “1600”). The dosage strength is also marked on the handle tag, the blister package and the carton. See blister package and carton for product information.

Dosage Strength; (fentanyl base) | Carton/Blister; Package Color | NDC Number
200 mcg | Gray | NDC 0093-7865-65
400 mcg | Blue | NDC 0093-7866-65
600 mcg | Orange | NDC 0093-7867-65
800 mcg | Purple | NDC 0093-7868-65
1200 mcg | Green | NDC 0093-7869-65
1600 mcg | Burgundy | NDC 0093-7870-65

Note: Colors are a secondary aid in product identification. Please be sure to confirm the printed dosage before dispensing.

Store at 20ºC to 25ºC (68ºF to 77ºF) with excursions permitted between 15°C and 30°C (59°F to 86°F) until ready to use. (See USP Controlled Room Temperature.) Protect OTFC from freezing and moisture. Do not use if the blister package has been opened.

Store OTFC securely and dispose of properly.

17 PATIENT COUNSELING INFORMATION

Advise the patient to read the FDA-approved patient labeling (Medication Guide).

Storage and Disposal of Unused and Used OTFC [see Medication Guide / Instructions for Use].

Because of the risks associated with accidental ingestion, misuse, and abuse, advise patients to store OTFC securely, out of sight and reach of children, and in a location not accessible by others, including visitors to the home. Inform patients that leaving OTFC unsecured can pose a deadly risk to others in the home [see Warnings and Precautions (5.1, 5.2), Drug Abuse and Dependence (9.2)].

Advise patients and caregivers that when medicines are no longer needed, they should be disposed of promptly. Inform patients that they can visit www.fda.gov/drugdisposal for a complete list of medicines recommended for disposal by flushing, as well as additional information on disposal of unused medicines.

Disposal of Used OTFC Units:
Instruct patients on proper disposal of completely used and partially used OTFC units as follows:

1. After consumption of the unit is complete and the matrix is totally dissolved, throw away the handle in a trash container that is out of the reach of children.
2. If any of the drug matrix remains on the handle, place the handle under hot running tap water until all of the drug matrix is dissolved, and then dispose of the handle in a place that is out of the reach of children.
3. Dispose of handles in the child-resistant container (as described in steps 1 and 2) at least once a day.

If the patient does not entirely consume the unit and the remaining drug cannot be immediately dissolved under hot running water, the patient or caregiver must temporarily store the OTFC unit in the specially provided child-resistant container out of the reach of children until proper disposal is possible.

Disposal of Unopened OTFC Units When No Longer Needed:
Patients and members of their household must be advised to dispose of any unopened units remaining from a prescription as soon as they are no longer needed.

To dispose of the unused OTFC units:

- Remove the OTFC unit from its blister package using scissors, and hold the OTFC by its handle over the toilet bowl.
- Using wire-cutting pliers cut off the drug matrix end so that it falls into the toilet.
- Dispose of the handle in a place that is out of the reach of children.
- Repeat steps 1, 2, and 3 for each OTFC unit. Flush the toilet twice after 5 units have been cut and deposited into the toilet.

Do not flush the entire OTFC units, OTFC handles, blister packages, or cartons down the toilet. Dispose of the handle where children cannot reach it.

Detailed instructions for the proper storage, administration, disposal, and important instructions for managing an overdose of OTFC are provided in the OTFC Medication Guide. Encourage patients to read this information in its entirety and give them an opportunity to have their questions answered.

In the event that a caregiver requires additional assistance in disposing of excess unusable units that remain in the home after a patient has expired, instruct them to call the toll-free number for Teva Pharmaceuticals (1-888-483-8279) or seek assistance from their local DEA office.

Addiction, Abuse, and Misuse

Inform patients that the use of OTFC, even when taken as recommended, can result in addiction, abuse, and misuse, which can lead to overdose and death [see Warnings and Precautions (5.1)]. Instruct patients not to share OTFC with others and to take steps to protect OTFC from theft or misuse.

Life-Threatening Respiratory Depression

Inform patients of the risk of life-threatening respiratory depression, including information that the risk is greatest when starting Oral Transmucosal Fentanyl Citrate (OTFC) or when the dosage is increased, and that it can occur even at recommended dosages.

Educate patients and caregivers on how to recognize respiratory depression and emphasize the importance of calling 911 or getting emergency medical help right away in the event of a known or suspected overdose [see Warnings and Precautions (5.2)].

Accidental Ingestion

- Healthcare providers and dispensing pharmacists must specifically question patients or caregivers about the presence of children in the home (on a full time or visiting basis) and counsel them regarding the dangers to children from inadvertent exposure [see Warnings and Precautions (5.3)].
- Inform patients that accidental ingestion, especially by children, may result in respiratory depression or death [see Warnings and Precautions (5.3)].
- Instruct patients to take steps to store OTFC securely and to dispose of unused OTFC [see Dosage and Administration (2.8), Warnings and Precautions (5.3, 5.7)].
- Instruct patients and caregivers to keep both used and unused OTFC out of the reach of children [see Warnings and Precautions (5.3)].
- Inform patients and their caregivers that, in the event that a unit is not completely consumed, it must be properly disposed as soon as possible [see Warnings and Precautions (5.3)].

OTFC Child Safety Kit
Provide patients and their caregivers who have children in the home or visiting with an OTFC Child Safety Kit, which contains educational materials and safe interim storage containers to help patients store OTFC and other medicines out of the reach of children. To obtain a supply of Child Safety Kits, health care professionals can call 1-888-534-3119.

Interactions with Benzodiazepines and Other CNS Depressants

Inform patients and caregivers that potentially fatal additive effects may occur if OTFC is used with benzodiazepines or other CNS depressants, including alcohol (e.g., non-benzodiazepine sedative/hypnotics, anxiolytics, tranquilizers, muscle relaxants, general anesthetics, antipsychotics, gabapentinoids [gabapentin or pregabalin], and other opioids), and not to use these concomitantly unless supervised by a healthcare provider [see Warnings and Precautions (5.4), Drug Interactions (7)].

Patient Access to an Opioid Overdose Reversal Agent for the Emergency Treatment of Opioid Overdose

Inform patients and caregivers about opioid overdose reversal agents (e.g., naloxone, nalmefene). Discuss the importance of having access to an opioid overdose reversal agent, especially if the patient has risk factors for overdose (e.g., concomitant use of CNS depressants, a history of opioid use disorder, or prior opioid overdose) or if there are household members (including children) or other close contacts at risk for accidental ingestion or opioid overdose.

Discuss with the patient the options for obtaining an opioid overdose reversal agent (e.g., prescription, over-the-counter, or as part of a community-based program) [see Dosage and Administration (2.2), Warnings and Precautions (5.4)].

Educate patients and caregivers on how to recognize the signs and symptoms of an overdose.

Explain to patients and caregivers that the effects of opioid overdose reversal agents like naloxone and nalmefene are temporary, and that they must call 911 or get emergency medical help right away in all cases of known or suspected opioid overdose, even if an opioid overdose reversal agent is administered [see Overdosage (10)].

Advise patients and caregivers:

- how to treat with their overdose reversal agent in the event of an opioid overdose
- to tell family and friends about their opioid overdose reversal agent, and to keep it in a place where family and friends can access it in an emergency
- to read the Patient Information (or other educational material) that will come with their opioid overdose reversal agent. Emphasize the importance of doing this before an opioid emergency happens, so the patient and caregiver will know what to do.

Transmucosal Immediate-Release Fentanyl (TIRF) REMS

OTFC is available only through a restricted program called the Transmucosal Immediate Release Fentanyl (TIRF) REMS [see Warnings and Precautions (5.7)]. Inform the patient of the following notable requirements:

- Outpatients must be enrolled in the REMS program
- Patients must be opioid-tolerant to receive OTFC

OTFC is available only from certified pharmacies participating in this program. Therefore, provide patients with the telephone number and website for information on how to obtain the product.

Pharmacies, outpatients, and healthcare professionals who prescribe to outpatients are required to enroll in the program. Inpatient pharmacies must develop policies and procedures to verify opioid tolerance in inpatients who require OTFC while hospitalized [see Warnings and Precautions (5.7)].

Hyperalgesia and Allodynia

Inform patients and caregivers not to increase opioid dosage without first consulting a clinician. Advise patients to seek medical attention if they experience symptoms of hyperalgesia, including worsening pain, increased sensitivity to pain, or new pain [see Warnings and Precautions (5.9), Adverse Reactions (6.2)].

Serotonin Syndrome

Inform patients that opioids could cause a rare but potentially life-threatening condition called serotonin syndrome resulting from concomitant administration of serotonergic drugs. Warn patients of the symptoms of serotonin syndrome and to seek medical attention right away if symptoms develop. Instruct patients to inform their healthcare providers if they are taking, or plan to take serotonergic medications [see Warnings and Precautions (5.10), Drug Interactions (7)].

MAOI Interaction

Inform patients to avoid taking OTFC while using any drugs that inhibit monoamine oxidase. Patients should not start MAOIs while taking OTFC [see Warnings and Precautions (5.10), Drug Interactions (7)].

Important Administration Instructions [see Dosage and Administration (2)]

- Instruct patients not to take OTFC for acute pain, postoperative pain, pain from injuries, headache, migraine or any other short-term pain, even if they have taken other opioid analgesics for these conditions.
- Instruct patients on the meaning of opioid tolerance and that OTFC is only to be used as a supplemental pain medication for patients with pain requiring around-the-clock opioids, who have developed tolerance to the opioid medication, and who need additional opioid treatment of breakthrough pain episodes.
- Instruct patients that, if they are not taking an opioid medication on a scheduled basis (around-the-clock), they should not take OTFC.
- Instruct patients that, if the breakthrough pain episode is not relieved 15 minutes after finishing the OTFC unit, they may take only one additional unit of OTFC using the same strength for that episode. Thus, patients should take no more than two units of OTFC for any breakthrough pain episode.
- Instruct patients that they MUST wait at least 4 hours before treating another episode of breakthrough pain with OTFC.
- Instruct patients NOT to share OTFC and that sharing OTFC with anyone else could result in the other individual’s death due to overdose.
- Make patients aware that OTFC contains fentanyl which is a strong pain medication similar to hydromorphone, methadone, morphine, oxycodone, and oxymorphone.
- Caution patients to talk to their healthcare provider if breakthrough pain is not alleviated or worsens after taking OTFC.
- Instruct patients to use OTFC exactly as prescribed by their healthcare provider and not to take OTFC more often than prescribed.

Driving or Operating Heavy Machinery

Inform patients that OTFC may impair the ability to perform potentially hazardous activities such as driving a car or operating heavy machinery. Advise patients not to perform such tasks until they know how they will react to the medication [see Warnings and Precautions (5.17)].

Constipation

Advise patients of the potential for severe constipation, including management instructions and when to seek medical attention [see Adverse Reactions (6), Clinical Pharmacology (12.2)].

Dental Decay

Because each OTFC unit contains approximately 2 grams of sugar (hydrated dextrates), frequent consumption may increase the risk of dental decay. The occurrence of dry mouth associated with the use of opioid medications (such as fentanyl) may add to this risk.

Post-marketing reports of dental decay have been received in patients taking OTFC [see Adverse Reactions (6.2)]. In some of these patients, dental decay occurred despite reported routine oral hygiene. As dental decay in cancer patients may be multi-factorial, patients using OTFC should consult their dentist to ensure appropriate oral hygiene.

Adrenal Insufficiency

Inform patients that opioids could cause adrenal insufficiency, a potentially life-threatening condition. Adrenal insufficiency may present with non-specific symptoms and signs such as nausea, vomiting, anorexia, fatigue, weakness, dizziness, and low blood pressure. Advise patients to seek medical attention if they experience a constellation of these symptoms [see Warnings and Precautions (5.12)].

Hypotension

Inform patients that OTFC may cause orthostatic hypotension and syncope. Instruct patients how to recognize symptoms of low blood pressure and how to reduce the risk of serious consequences should hypotension occur (e.g., sit or lie down, carefully rise from a sitting or lying position) [see Warnings and Precautions (5.13)].

Anaphylaxis

Inform patients that anaphylaxis has been reported with ingredients contained in OTFC. Advise patients how to recognize such a reaction and when to seek medical attention [see Contraindications (4), Adverse Reactions (6)].

Pregnancy

Neonatal Opioid Withdrawal Syndrome
Inform patients that use of OTFC for an extended period of time during pregnancy can result in neonatal opioid withdrawal syndrome, which may be life-threatening if not recognized and treated [see Warnings and Precautions (5.8), Use in Specific Populations (8.1)].

Embryo-Fetal Toxicity
Inform female patients of reproductive potential that OTFC can cause fetal harm and to inform their healthcare provider of a known or suspected pregnancy [see Use in Specific Populations (8.1)].

Lactation

Advise nursing mothers to carefully observe infants for increased sleepiness (more than usual), breathing difficulties, or limpness. Instruct nursing mothers to seek immediate medical care if they notice these signs [see Use in Specific Populations (8.2)].

Infertility

Inform patients that use of opioids for an extended period of time may cause reduced fertility. It is not known whether these effects on fertility are reversible [see Use in Specific Populations (8.3)].

Diabetic Patients

Advise diabetic patients that OTFC contains approximately 2 grams of sugar per unit.

Dispense with Medication Guide available at: www.tevausa.com/medguides

OTF-018

Distributed By:
Teva Pharmaceuticals USA, Inc.
Parsippany, NJ 07054

©2026 Cephalon, LLC.

MEDICATION GUIDE

Dispense with Medication Guide available at: www.tevausa.com/medguides

Medication Guide

Oral Transmucosal Fentanyl Citrate (OTFC)

(fentanyl citrate) oral transmucosal lozenge, CII

IMPORTANT:

Do not use Oral Transmucosal Fentanyl Citrate (OTFC) unless you are regularly using another opioid pain medicine around-the-clock for at least one week or longer for your cancer pain and your body is used to these medicines (this means that you are opioid tolerant). You can ask your healthcare provider if you are opioid tolerant.

Keep OTFC in a safe place away from children.

Get emergency medical help right away if:

- a child takes OTFC. OTFC can cause an overdose and death in any child who takes it.
- an adult who has not been prescribed OTFC uses it.
- an adult who is not already taking opioids around-the-clock, uses OTFC.

These are medical emergencies that can cause death. If possible, remove OTFC from the mouth.

Oral Transmucosal Fentanyl Citrate (OTFC) is:

- A strong prescription pain medicine that contains an opioid (narcotic) that is used to manage breakthrough pain in adults (16 years of age and older) with cancer who are already routinely taking other opioid pain medicines around-the-clock for cancer pain. OTFC is started only after you have been taking other opioid pain medicines and your body has become used to them (you are opioid tolerant). Do not use OTFC if you are not opioid tolerant.
- An opioid pain medicine that can put you at risk for overdose and death. Even if you take your dose correctly as prescribed you are at risk for opioid addiction, abuse, and misuse that can lead to death.

Important information about Oral Transmucosal Fentanyl Citrate (OTFC):

- Get emergency help or call 911 right away if you take too much OTFC (overdose). When you first start taking OTFC, when your dose is changed, or if you take too much (overdose), serious or life-threatening breathing problems that can lead to death may occur. Ask your healthcare provider about medicines like naloxone or nalmefene that can be used in an emergency to reverse an opioid overdose.
- Taking OTFC with other medicines that may make you sleepy, such as other pain medicines, gabapentinoids (gabapentin or pregabalin), anti-depressants, sleeping pills, anti-anxiety medicines, antihistamines, or tranquilizers, or with alcohol or street drugs can cause severe drowsiness, confusion, breathing problems, coma, and death.
- Never give anyone else your OTFC. They could die from taking it. Selling or giving away OTFC is against the law.
- Store OTFC securely, out of sight and reach of children, and in a location not accessible by others, including visitors to the home.
- If you stop taking your around-the-clock opioid pain medicine for your cancer pain, you must stop using OTFC. You may no longer be opioid tolerant. Talk to your healthcare provider about how to treat your pain.
- OTFC is available only through a program called the Transmucosal Immediate Release Fentanyl (TIRF) Risk Evaluation and Mitigation Strategy (REMS). To receive OTFC, you must:
  - talk to your healthcare provider
  - understand the benefits and risks of OTFC
  - agree to all of the instructions
  - sign the Patient Enrollment Form
- OTFC is only available at pharmacies that are part of the TIRF REMS. Your healthcare provider can help you locate a pharmacy closest to your home where you can have your OTFC prescription filled.
- Know the medicines you take. Keep a list of them to show your healthcare provider and pharmacist when you get a new medicine.

Do not take Oral Transmucosal Fentanyl Citrate (OTFC) if:

- You are not opioid tolerant. Opioid tolerant means that you are already taking other opioid pain medicines around-the-clock for at least one week or longer for your cancer pain, and your body is used to these medicines.
- You have severe asthma, trouble breathing, or other lung problems.
- You have a bowel blockage or have narrowing of the stomach or intestines.
- You are allergic to any of the ingredients in OTFC. See the end of this Medication Guide for a complete list of ingredients in OTFC.
- You have short-term pain that you would expect to go away in a few days, such as:
  - pain after surgery
  - headache or migraine
  - dental pain

Before taking Oral Transmucosal Fentanyl Citrate (OTFC), tell your healthcare provider if you have a history of:

- troubled breathing or lung problems such as asthma, wheezing, or shortness of breath
- head injury, seizures
- slow heart rate or other heart problems
- low blood pressure
- mental problems [including major depression, schizophrenia or hallucinations (seeing or hearing things that are not there)]
- problems urinating
- liver, kidney, thyroid problems
- pancreas or gallbladder problems
- abuse of street or prescription drugs, alcohol addiction, opioid overdose, or mental health problems
- diabetes. Each OTFC unit contains about 1/2 teaspoon (2 grams) of sugar.

Tell your healthcare provider if you are:

- noticing your pain getting worse. If your pain gets worse after you take OTFC, do not take more OTFC without first talking to your healthcare provider. Talk to your healthcare provider if the pain you have increases, if your feel more sensitive to pain, or if you have new pain after taking OTFC.
- pregnant or planning to become pregnant. Use of OTFC for an extended period of time during pregnancy can cause withdrawal symptoms in your newborn baby that could be life-threatening if not recognized and treated.
- breastfeeding. OTFC passes into breast milk and may harm your baby. Carefully observe infants for increased sleepiness (more than usual), breathing difficulties, or limpness. Seek immediate medical care if you notice these signs.
- living in a household where there are small children or someone who has abused street or prescription drugs.
- taking prescription over-the-counter medicines, vitamins, or herbal supplements. Taking OTFC with certain other medicines can cause serious side effects that could lead to death.

When taking Oral Transmucosal Fentanyl Citrate (OTFC):

- Do not change your dose. Take OTFC exactly as prescribed by your healthcare provider.
- Your healthcare provider will change the dose until you and your healthcare provider find the right dose for you.
- See the detailed Patient Instructions for Use at the end of this Medication Guide for information about how to use OTFC.
- Finish the unit completely in 15 minutes to get the most relief. If you finish OTFC too quickly, you will swallow more of the medicine and get less relief.
- Do not bite or chew. You will get less relief for your breakthrough cancer pain.
- You may drink some water before using OTFC but you should not drink or eat anything while using OTFC.
- You must not use more than 2 units of OTFC during each episode of breakthrough cancer pain:
  - Use 1 unit for an episode of breakthrough cancer pain. Finish the unit over 15 minutes.
  - If your breakthrough cancer pain is not relieved 15 minutes after you finished the OTFC unit, use only 1 more unit of OTFC at this time.
  - If your breakthrough pain does not get better after the second unit of OTFC, call your healthcare provider for instructions. Do not use another unit of OTFC at this time.
- Wait at least 4 hours before treating a new episode of breakthrough cancer pain with OTFC.
- It is important for you to keep taking your around-the-clock opioid pain medicine.
- Talk to your healthcare provider if your dose of OTFC does not relieve your breakthrough cancer pain. Your healthcare provider will decide if your dose of OTFC needs to be changed.
- Talk to your healthcare provider if you have more than 4 episodes of breakthrough cancer pain per day. The dose of your around-the-clock opioid pain medicine may need to be adjusted.
- If you begin to feel dizzy, sick to your stomach, or very sleepy before OTFC is completely dissolved, remove OTFC from your mouth.
- Do not stop taking OTFC without talking to your healthcare provider. You could become sick with uncomfortable withdrawal symptoms because your body has become used to these medicines. Physical dependency is not the same as drug addiction.
- After you stop taking, or when OTFC is no longer needed, see “How should I dispose of Oral Transmucosal Fentanyl Citrate (OTFC) units when they are no longer needed?” for proper disposal of OTFC.
- Dispose of expired, unwanted, or unused OTFC by following the “How should I dispose of Oral Transmucosal Fentanyl Citrate (OTFC) units when they are no longer needed?” sections of this Medication Guide below. Visit www.fda.gov/drugdisposal for additional information on disposal of unused medicines.
- DO NOT Drive or operate heavy machinery until you know how OTFC affects you. OTFC can make you sleepy, dizzy, or lightheaded.
- DO NOT Drink alcohol or use prescription or over-the-counter medicines that contain alcohol. Using products containing alcohol during treatment with OTFC may cause you to overdose and die.
- DO NOT Switch from OTFC to other medicines that contain fentanyl without talking to your healthcare provider. The amount of fentanyl in a dose of OTFC is not the same as the amount of fentanyl in other medicines that contain fentanyl. Your healthcare provider will prescribe a starting dose of OTFC that may be different than other fentanyl containing medicines you may have been taking.

The possible side effects of Oral Transmucosal Fentanyl Citrate (OTFC):

- constipation, nausea, sleepiness, vomiting, tiredness, headache, dizziness, abdominal pain, weakness, anxiety, depression, rash, trouble sleeping. Call your healthcare provider if you have any of these symptoms and they are severe.
- Decreased blood pressure. This can make you feel dizzy or lightheaded if you get up too fast from sitting or lying down.
- OTFC contains sugar. Cavities and tooth decay can happen in people taking OTFC. When taking OTFC, you should talk to your dentist about proper care of your teeth.

Get emergency medical help or call 911 right away if you have:

- trouble breathing, shortness of breath, fast heartbeat, chest pain, swelling of your face, tongue, or throat, extreme drowsiness, light-headedness when changing positions, feeling faint, agitation, high body temperature, trouble walking, stiff muscles, or mental changes such as confusion.
- These symptoms can be a sign that you have used too much OTFC or the dose is too high for you. These symptoms may lead to serious problems or death if not treated right away. If you have any of these symptoms, do not use any more OTFC until you have talked to your healthcare provider.

These are not all the possible side effects of OTFC. Call your doctor for medical advice about side effects. You may report side effects to FDA at 1-800-FDA-1088. For more information go to dailymed.nlm.nih.gov

How should I store Oral Transmucosal Fentanyl Citrate (OTFC)?

- Always keep OTFC in a safe place away from children and from anyone for whom it has not been prescribed. Protect OTFC from theft.
  - You can use the OTFC Child Safety Kit to help you store OTFC and your other medicines out of the reach of children. It is very important that you use the items in the OTFC Child Safety Kit to help protect the children in your home or visiting your home.
  - If you were not offered a Child Safety Kit when you received your medicine, call 888-534-3119.

The OTFC Child Safety Kit contains important information on the safe storage and handling of OTFC.

The Child Safety Kit includes:

- A child-resistant lock that you use to secure the storage space where you keep OTFC (See Figure 1).

Figure 1

- A portable locking pouch for you to keep a small supply of OTFC nearby. The rest of your OTFC must be kept in a locked storage space.
  - Keep this pouch secured with its lock and keep it out of the reach and sight of children (See Figure 2).

Figure 2

- A child-resistant temporary storage bottle (See Figure 3).

Figure 3

- Store OTFC at room temperature, 59°F to 86°F (15°C to 30°C) until ready to use.
- Do not freeze OTFC.
- Keep OTFC in the original sealed child-resistant blister package. Do not open the blister package until you are ready to use OTFC.
- Keep OTFC dry.

How should I dispose of Oral Transmucosal Fentanyl Citrate (OTFC) units when they are no longer needed?

Disposing of OTFC units after use:

Partially used OTFC units may contain enough medicine to be harmful or fatal to a child or other adults who have not been prescribed OTFC. You must properly dispose of the OTFC handle right away after use even if there is little or no medicine left on it.

After you have finished the OTFC unit and the medicine is totally gone, throw the handle away in a place that is out of the reach of children.

If any medicine remains on the used OTFC unit after you have finished:

- Place the used OTFC unit under hot running water until the medicine is gone, and then throw the handle away out of the reach of children and pets (See Figure 4).

Figure 4

Temporary Storage of Used OTFC Units:

- If you did not finish the entire OTFC unit and you cannot dissolve the medicine under hot running water right away, put the used OTFC unit in the temporary storage bottle that you received in the OTFC Child Safety Kit. Push the used OTFC unit into the opening on the top until it falls completely into the bottle. Never leave unused or partially used OTFC units where children or pets can get to them (See Figure 5).

Figure 5

Disposing of Used OTFC Units from the Temporary Storage Bottle:

You must dispose of all used OTFC units in the temporary storage bottle at least one time each day, as follows:

1. To open the temporary storage bottle, push down on the cap until you are able to twist the cap to the left to remove it (See Figure 6).

Figure 6

2. Remove one OTFC unit from the temporary storage bottle. Hold the OTFC by its handle over the toilet bowl.
3. Using wire-cutting pliers, cut the medicine end off so that it falls into the toilet.
4. Throw the handle away in a place that is out of the reach of children.
5. Repeat these 3 steps for each OTFC handle that is in the storage bottle. There should not be more than 4 handles in the temporary storage bottle for 1 day.
6. Flush the toilet twice.

Do not flush entire unused OTFC units, OTFC handles, or blister packages down the toilet.

Disposing of unopened OTFC units: Dispose of any unopened OTFC units remaining from a prescription as soon as they are no longer needed, as follows:

1. Remove all OTFC from the locked storage space (See Figure 7).

Figure 7

2. Remove one OTFC unit from its blister package by using scissors to cut off the marked end and then peel back the blister backing (See Figures 8A and 8B).

Figure 8A Figure 8B
3. Hold OTFC by its handle over the toilet bowl. Use wire-cutting pliers to cut the medicine end off so that it falls into the toilet (See Figures 9A and 9B).

Figure 9A Figure 9B
4. Throw the handle away in a place that is out of the reach of children (See Figure 10).

Figure 10

5. Repeat steps 1 through 4 for each OTFC unit.
6. Flush the toilet twice after the medicine ends from 5 OTFC units have been cut off (See Figure 11). Do not flush more than 5 OTFC units at a time.

Figure 11

- Do not flush entire unused OTFC units, OTFC handles, or blister packages down the toilet.

If you need help with disposal of OTFC, call Teva Pharmaceuticals at 1-888-483-8279, or call your local Drug Enforcement Agency (DEA) office.

General information about Oral Transmucosal Fentanyl Citrate (OTFC)

Medicines are sometimes prescribed for purposes other than those listed in a Medication Guide. Use OTFC only for the purpose for which it was prescribed. Do not give OTFC to other people, even if they have the same symptoms you have. OTFC can harm other people and even cause death. Sharing OTFC is against the law.

This Medication Guide summarizes the most important information about OTFC. If you would like more information, talk with your healthcare provider or pharmacist. You can ask your pharmacist or healthcare provider for information about OTFC that is written for healthcare professionals.

For more information about the TIRF REMS Access program, go to www.TIRFREMSAccess.com or call 1-866-822-1483.

What are the ingredients of Oral Transmucosal Fentanyl Citrate (OTFC)?

Active Ingredient: fentanyl citrate

Inactive Ingredients: sugar, citric acid, dibasic sodium phosphate, artificial berry flavor, magnesium stearate, modified food starch and confectioner’s sugar.

Patient Instructions for Use

Before you use OTFC, it is important that you read the Medication Guide and these Patient Instructions for Use. Be sure that you read, understand, and follow these Patient Instructions for Use so that you use OTFC the right way. Ask your healthcare provider or pharmacist if you have any questions about the right way to use OTFC.

When you get an episode of breakthrough cancer pain, use the dose of OTFC prescribed by your healthcare provider as follows:

- You may drink some water before using OTFC but you should not drink or eat anything while using OTFC.
- Each unit of OTFC is sealed in its own blister package (See Figure 12). Do not open the blister package until you are ready to use OTFC.

Figure 12

- When you are ready to use OTFC, cut open the package using scissors. Peel back the blister backing, and remove the OTFC unit (See Figures 13A and 13B). The end of the unit printed with “FENTANYL” and the strength number of the unit (“200”, “400”, “600”, “800”, “1200”, or “1600”) is the medicine end that is to be placed in your mouth. Hold the OTFC unit by the handle (See Figure 14).

Figure 13A Figure 13B

Figure 14

1. Place the medicine end of the OTFC unit in your mouth between your cheeks and gums and actively suck on the medicine.
2. Move the medicine end of the OTFC unit around in your mouth, especially along the inside of your cheeks (See Figure 15).

Figure 15

3. Twirl the handle often.
4. Finish the OTFC unit completely over 15 minutes to get the most relief. If you finish OTFC too quickly, you will swallow more of the medicine and get less relief.
5. Do not bite or chew OTFC. You will get less relief for your breakthrough cancer pain.

- If you cannot finish all of the medicine on the OTFC unit and cannot dissolve the medicine under hot tap water right away, immediately put the OTFC unit in the temporary storage bottle for safe keeping (See Figure 16).
  - Push the OTFC unit into the opening on the top until it falls completely into the bottle. You must properly dispose of the OTFC unit as soon as you can.

Figure 16

See “How should I dispose of Oral Transmucosal Fentanyl Citrate (OTFC) units when they are no longer needed?” for proper disposal of OTFC.

Distributed by:

Teva Pharmaceuticals USA, Inc. call 1-888-483-8279
Parsippany, NJ 07054

OTFMG-018
©2026 Cephalon, LLC.

Printed in USA

This Medication Guide has been approved by the U.S. Food and Drug Administration. Revised: 1/2026

Package/Label Display Panel

NDC 0093-7865-65
Oral Transmucosal Fentanyl Citrate (OTFC) CII
equivalent to 200 mcg fentanyl base

Only for patients already taking around-the-clock opioids (narcotics) such as fentanyl or morphine.

PATIENTS MUST BE TOLERANT TO AROUND-THE-CLOCK OPIOID THERAPY
DO NOT SUBSTITUTE OTFC FOR OTHER FENTANYL PRODUCTS

WARNING: Keep out of the reach of children.

- Accidental ingestion of this medicine by a child could be harmful or fatal.
- Partially consumed OTFC must be disposed of properly.
- Read enclosed OTFC Medication Guide and consult your physician for important warnings and directions.
- Call 1-888-534-3119 for a free OTFC Child Safety Kit with important additional information about safe use, storage, and disposal of this medicine.

Rx only
30 Units
TEVA

Package/Label Display Panel

NDC 0093-7866-65
Oral Transmucosal Fentanyl Citrate (OTFC) CII
equivalent to 400 mcg fentanyl base

Only for patients already taking around-the-clock opioids (narcotics) such as fentanyl or morphine.

PATIENTS MUST BE TOLERANT TO AROUND-THE-CLOCK OPIOID THERAPY
DO NOT SUBSTITUTE OTFC FOR OTHER FENTANYL PRODUCTS

WARNING: Keep out of the reach of children.

- Accidental ingestion of this medicine by a child could be harmful or fatal.
- Partially consumed OTFC must be disposed of properly.
- Read enclosed OTFC Medication Guide and consult your physician for important warnings and directions.
- Call 1-888-534-3119 for a free OTFC Child Safety Kit with important additional information about safe use, storage, and disposal of this medicine.
  Rx only
  30 Units
  TEVA

Package/Label Display Panel

NDC 0093-7867-65
Oral Transmucosal Fentanyl Citrate (OTFC) CII
equivalent to 600 mcg fentanyl base

Only for patients already taking around-the-clock opioids (narcotics) such as fentanyl or morphine.

PATIENTS MUST BE TOLERANT TO AROUND-THE-CLOCK OPIOID THERAPY

DO NOT SUBSTITUTE OTFC FOR OTHER FENTANYL PRODUCTS

WARNING: Keep out of the reach of children.

- Accidental ingestion of this medicine by a child could be harmful or fatal.
- Partially consumed OTFC must be disposed of properly.
- Read enclosed OTFC Medication Guide and consult your physician for important warnings and directions.
- Call 1-888-534-3119 for a free OTFC Child Safety Kit with important additional information about safe use, storage, and disposal of this medicine.
  Rx only
  30 Units

TEVA

Package/Label Display Panel

NDC 0093-7868-65
Oral Transmucosal Fentanyl Citrate (OTFC) CII
equivalent to 800 mcg fentanyl base

Only for patients already taking around-the-clock opioids (narcotics) such as fentanyl or morphine.

PATIENTS MUST BE TOLERANT TO AROUND-THE-CLOCK OPIOID THERAPY
DO NOT SUBSTITUTE OTFC FOR OTHER FENTANYL PRODUCTS

WARNING: Keep out of the reach of children.

- Accidental ingestion of this medicine by a child could be harmful or fatal.
- Partially consumed OTFC must be disposed of properly.
- Read enclosed OTFC Medication Guide and consult your physician for important warnings and directions.
- Call 1-888-534-3119 for a free OTFC Child Safety Kit with important additional information about safe use, storage, and disposal of this medicine.
  Rx only
  30 Units
  TEVA

Package/Label Display Panel

NDC 0093-7869-65
Oral Transmucosal Fentanyl Citrate (OTFC) CII
equivalent to 1200 mcg fentanyl base

Only for patients already taking around-the-clock opioids (narcotics) such as fentanyl or morphine.

PATIENTS MUST BE TOLERANT TO AROUND-THE-CLOCK OPIOID THERAPY
DO NOT SUBSTITUTE OTFC FOR OTHER FENTANYL PRODUCTS

WARNING: Keep out of the reach of children.

- Accidental ingestion of this medicine by a child could be harmful or fatal.
- Partially consumed OTFC must be disposed of properly.
- Read enclosed OTFC Medication Guide and consult your physician for important warnings and directions.
- Call 1-888-534-3119 for a free OTFC Child Safety Kit with important additional information about safe use, storage, and disposal of this medicine.
  Rx only
  30 Units
  TEVA

Package/Label Display Panel

NDC 0093-7870-65
Oral Transmucosal Fentanyl Citrate (OTFC) CII
equivalent to 1600 mcg fentanyl base

Only for patients already taking around-the-clock opioids (narcotics) such as fentanyl or morphine.

PATIENTS MUST BE TOLERANT TO AROUND-THE-CLOCK OPIOID THERAPY
DO NOT SUBSTITUTE OTFC FOR OTHER FENTANYL PRODUCTS

WARNING: Keep out of the reach of children.

- Accidental ingestion of this medicine by a child could be harmful or fatal.
- Partially consumed OTFC must be disposed of properly.
- Read enclosed OTFC Medication Guide and consult your physician for important warnings and directions.
- Call 1-888-534-3119 for a free OTFC Child Safety Kit with important additional information about safe use, storage, and disposal of this medicine.
  Rx only
  30 Units
  TEVA